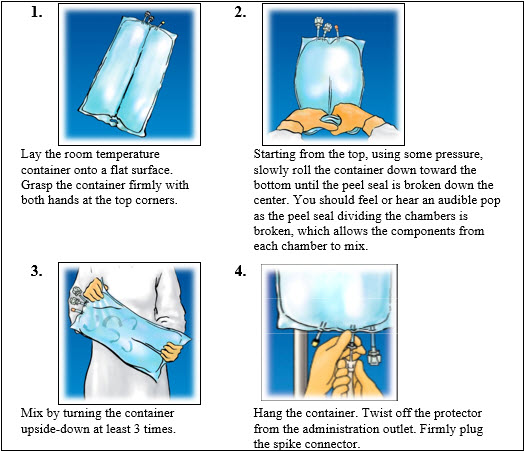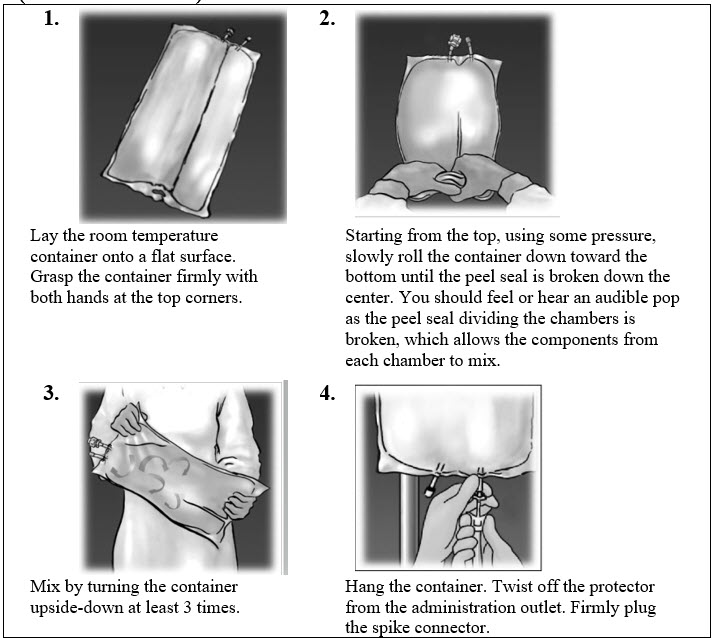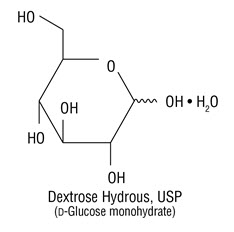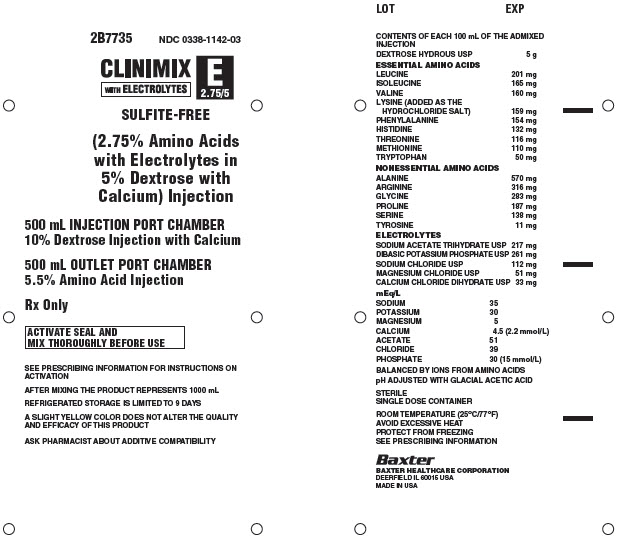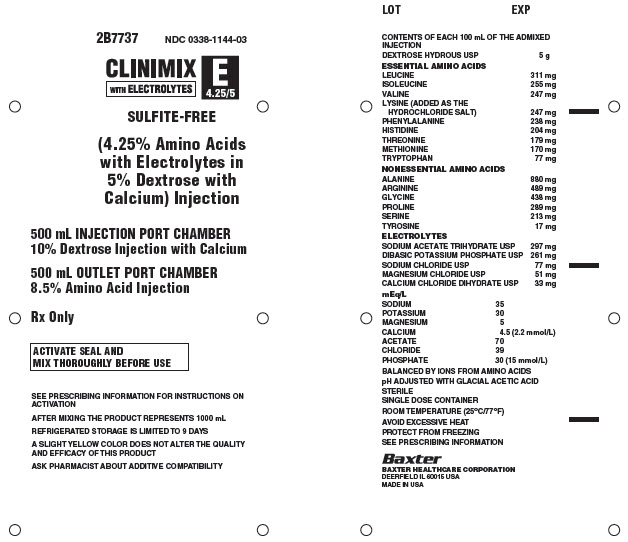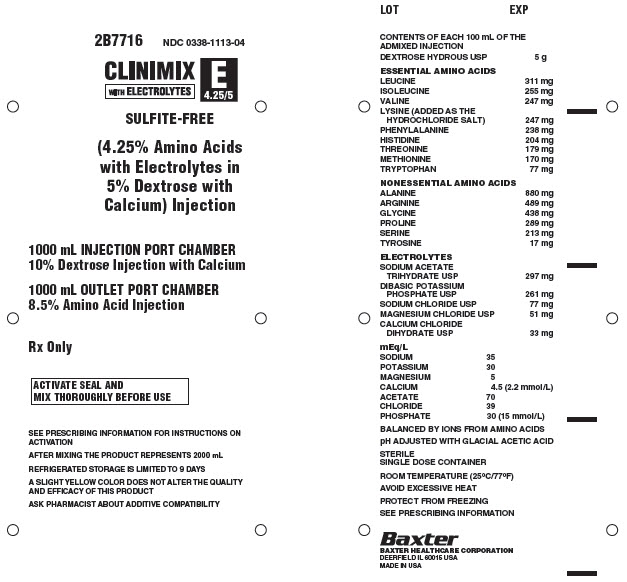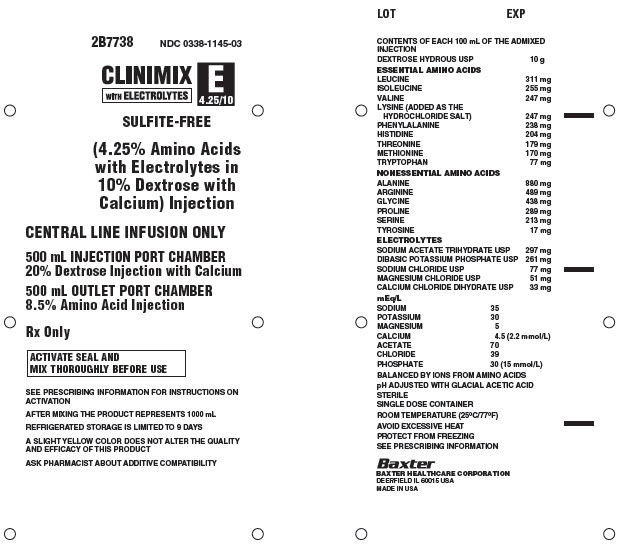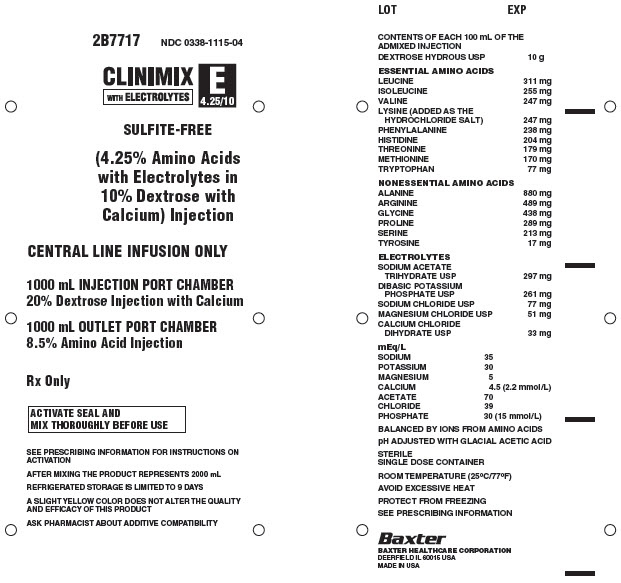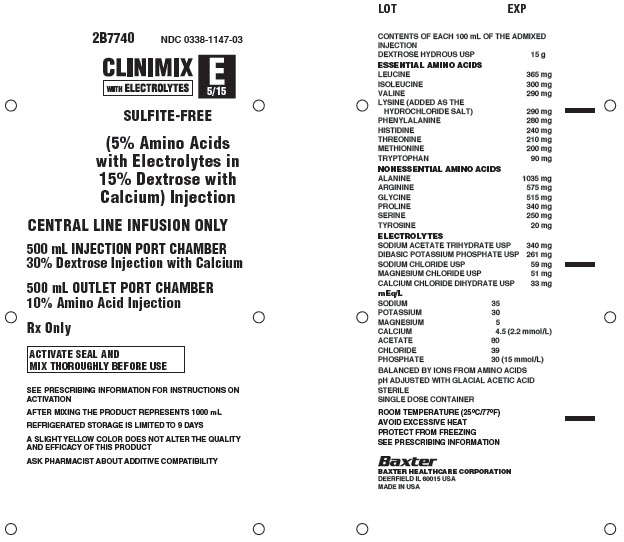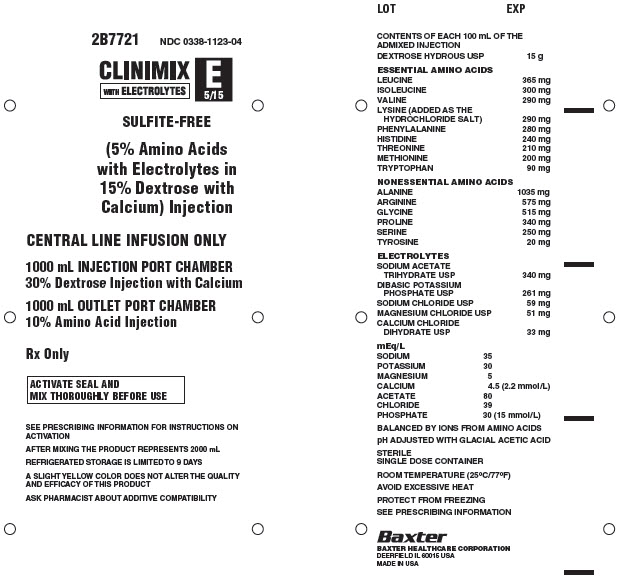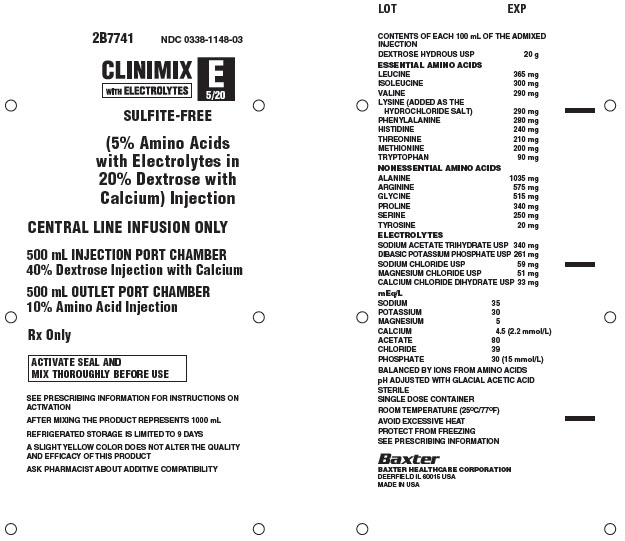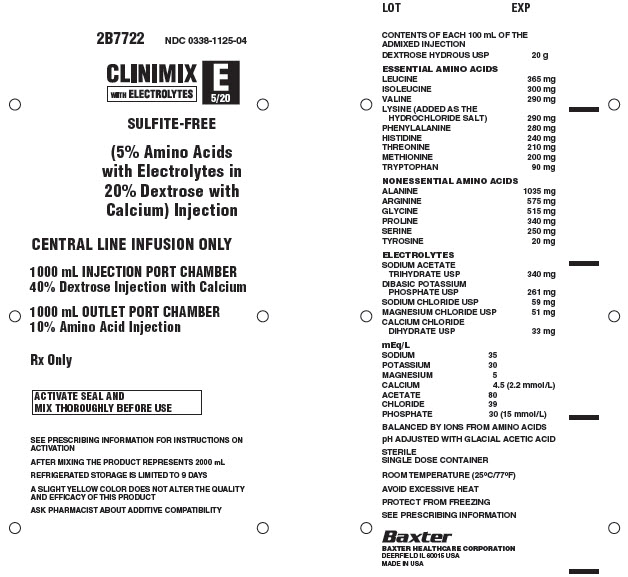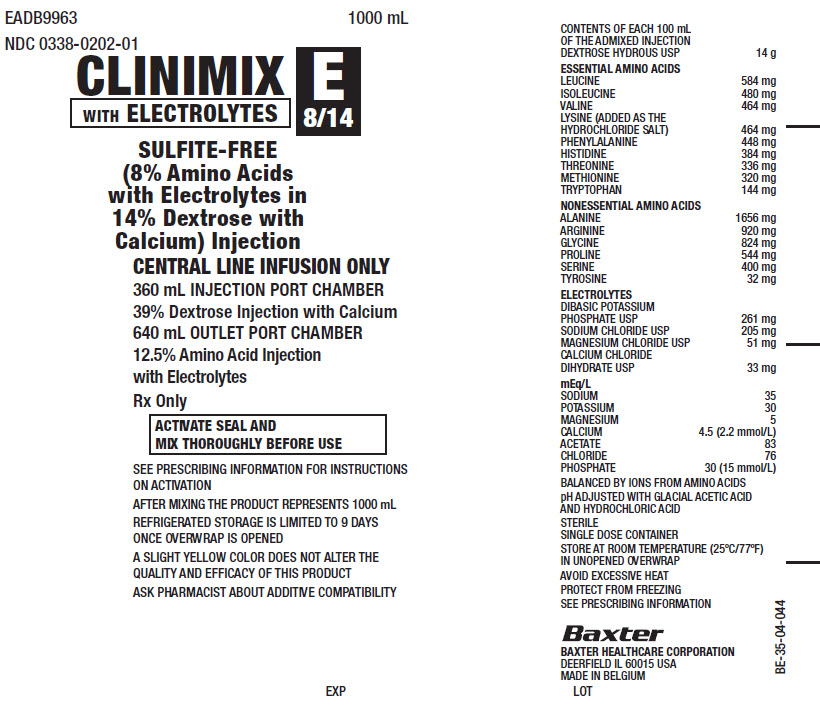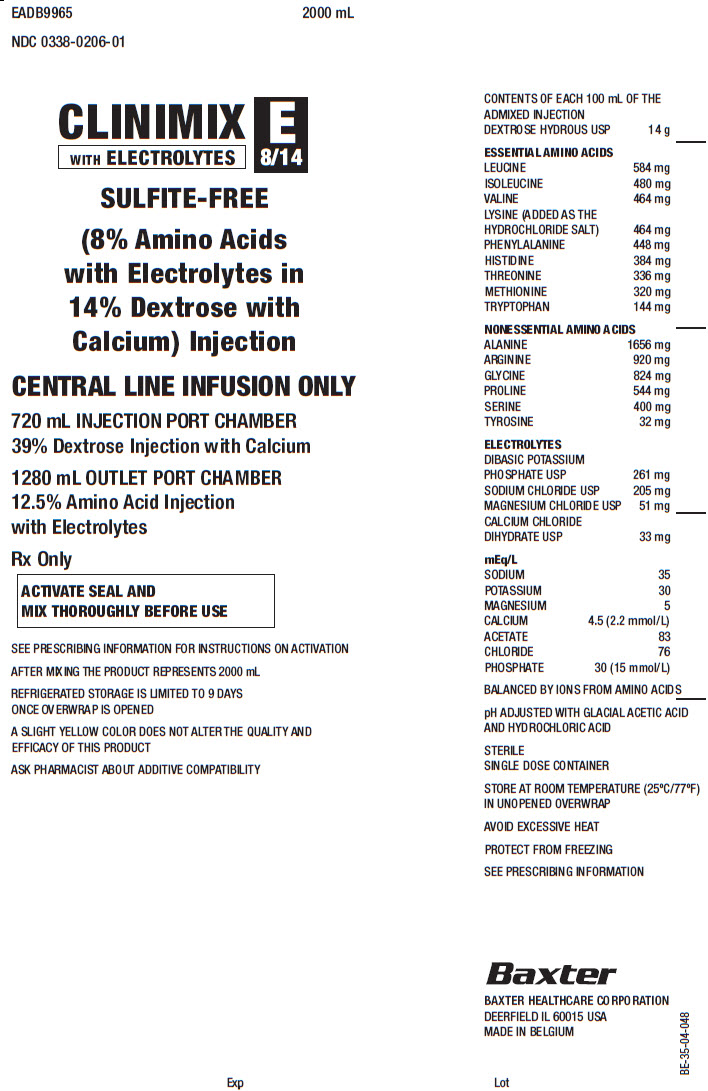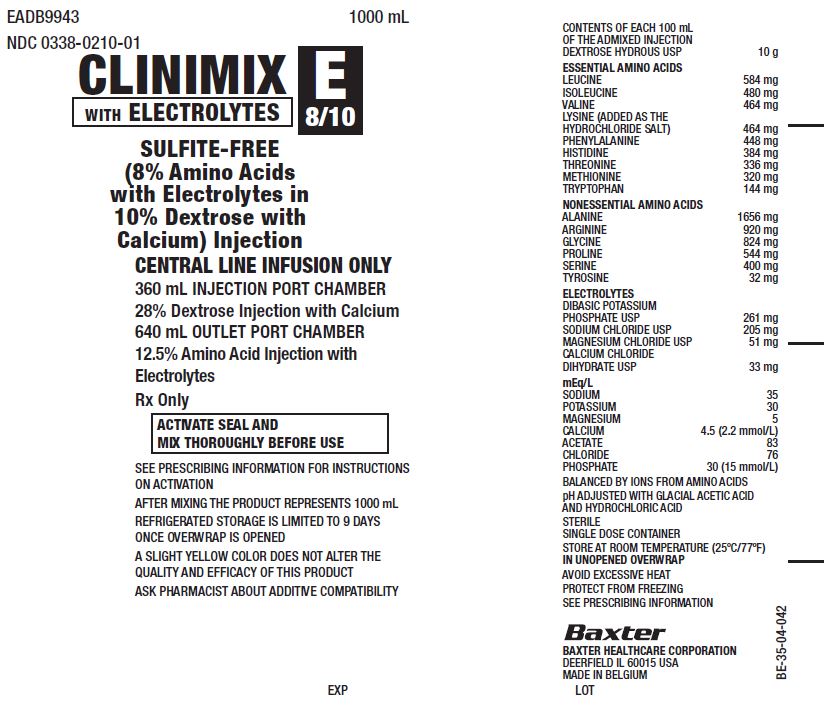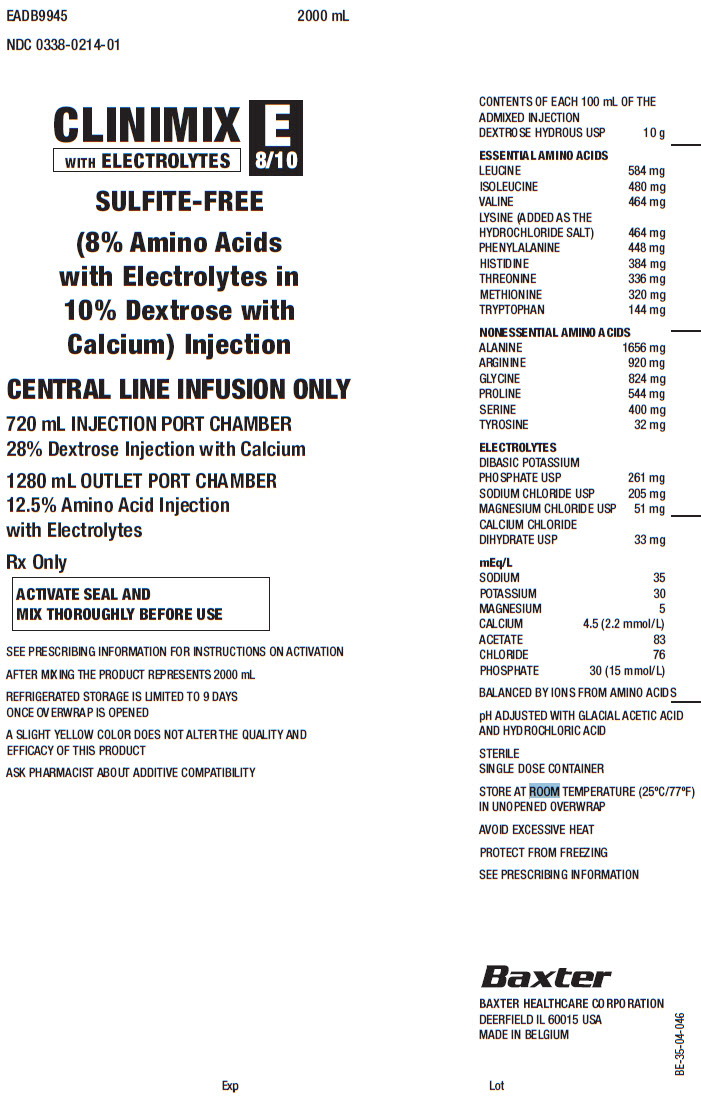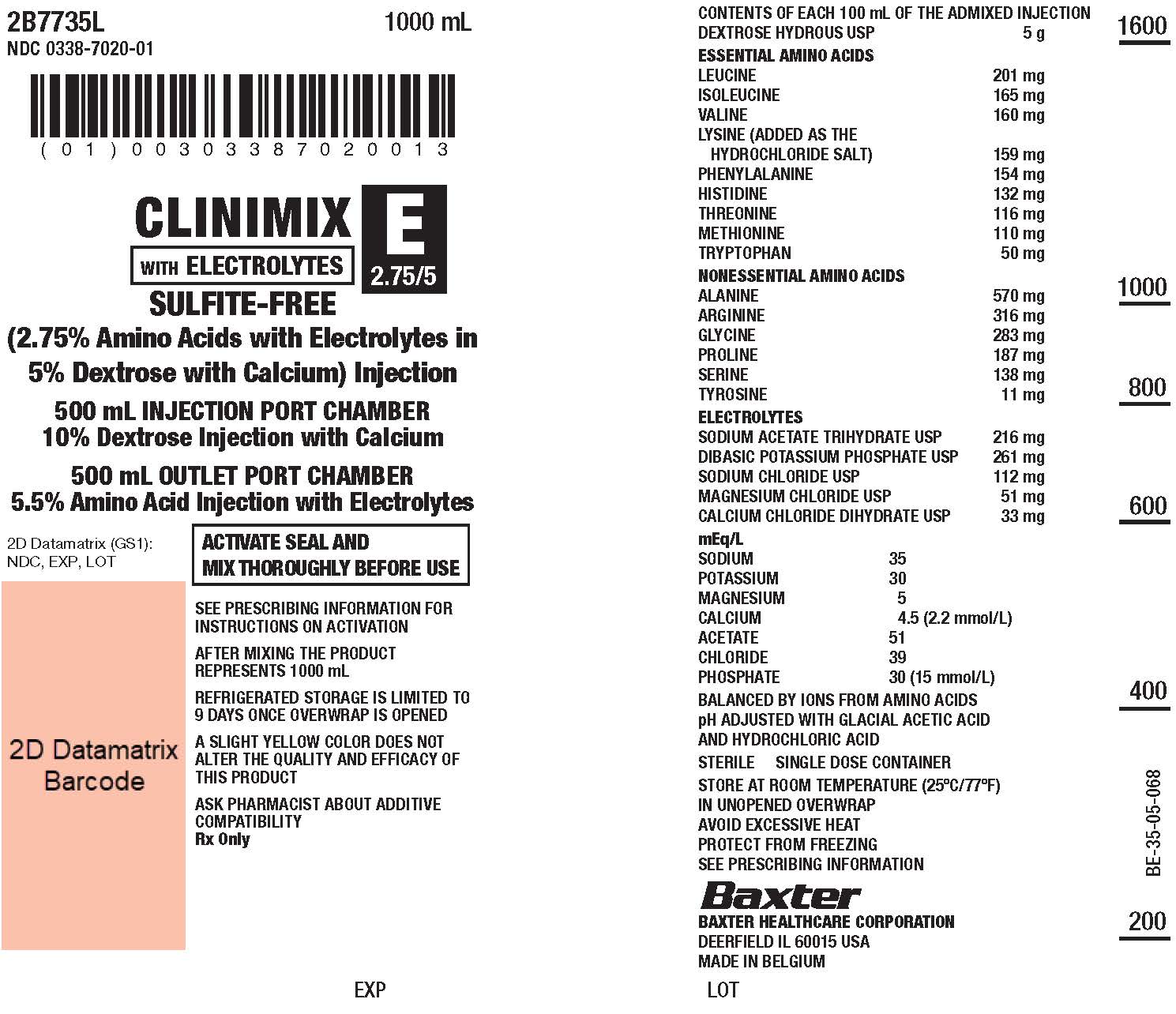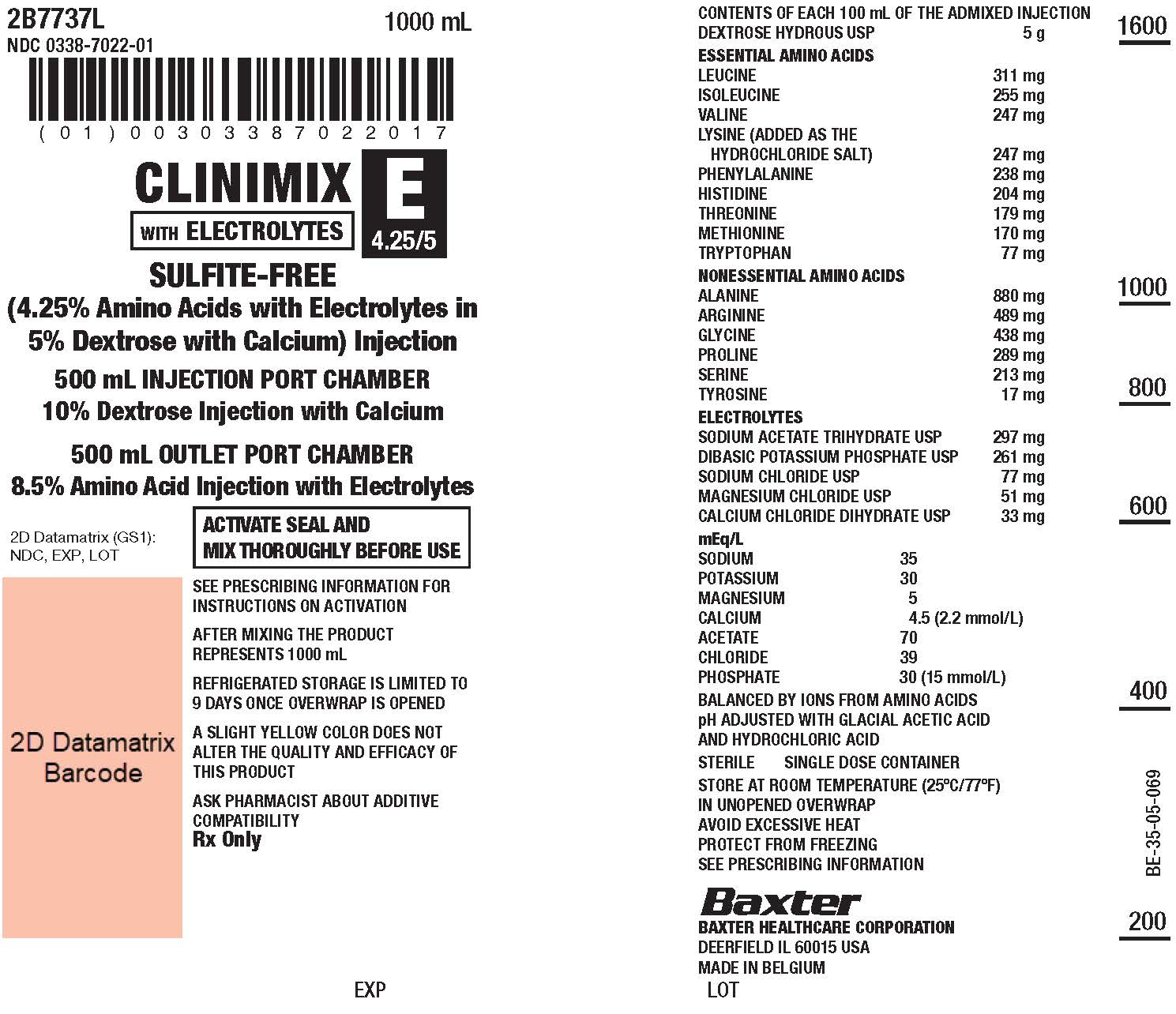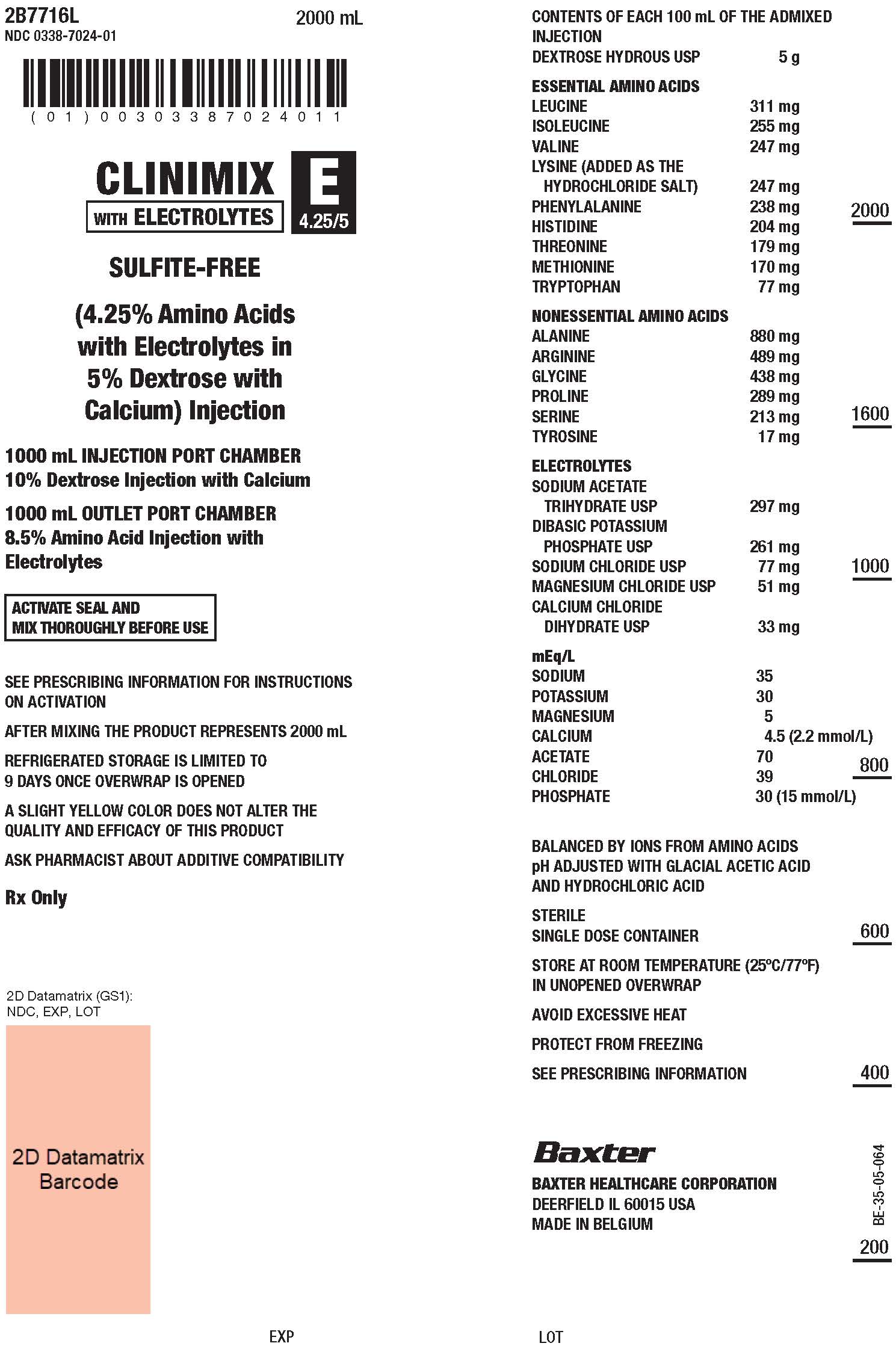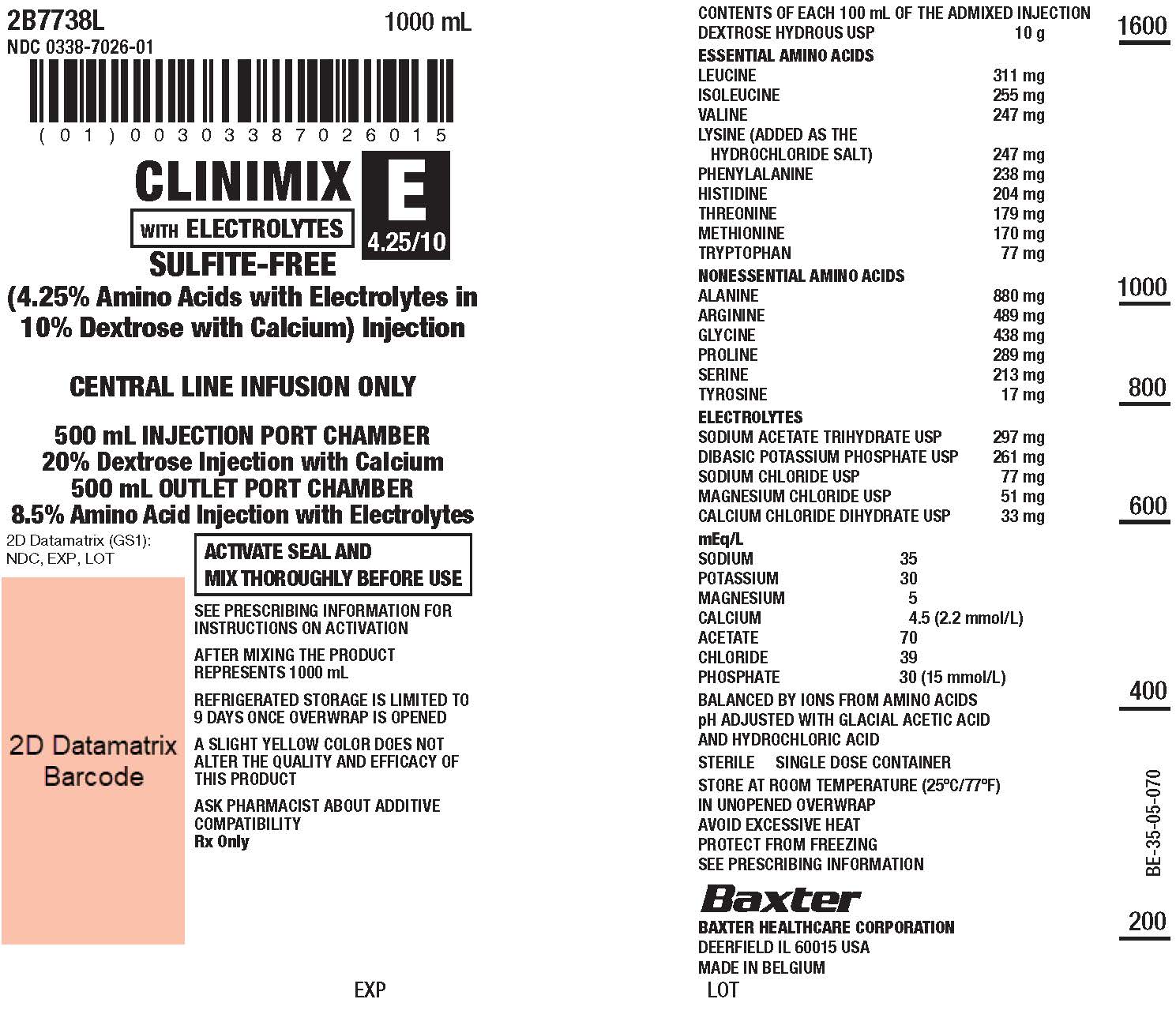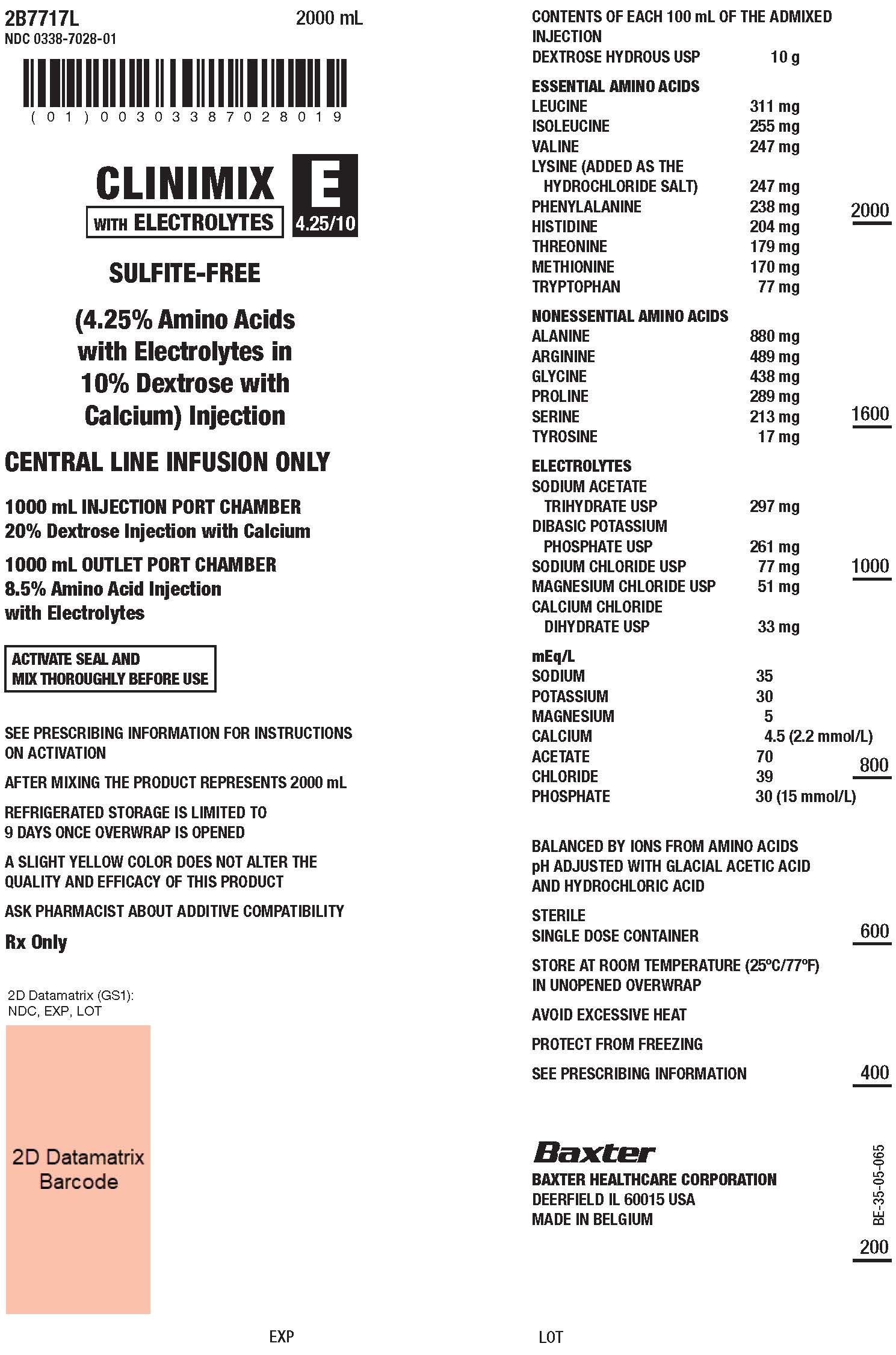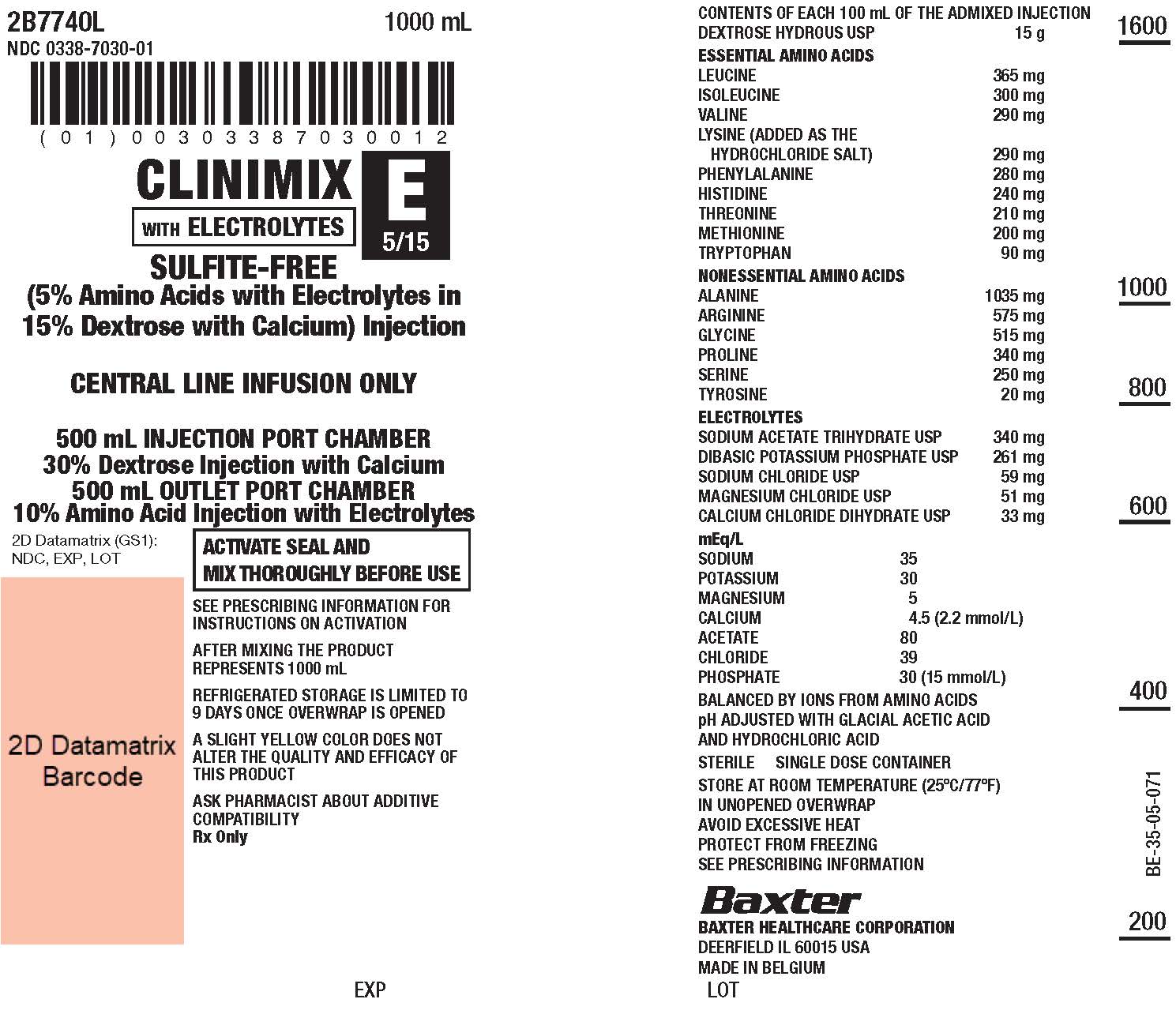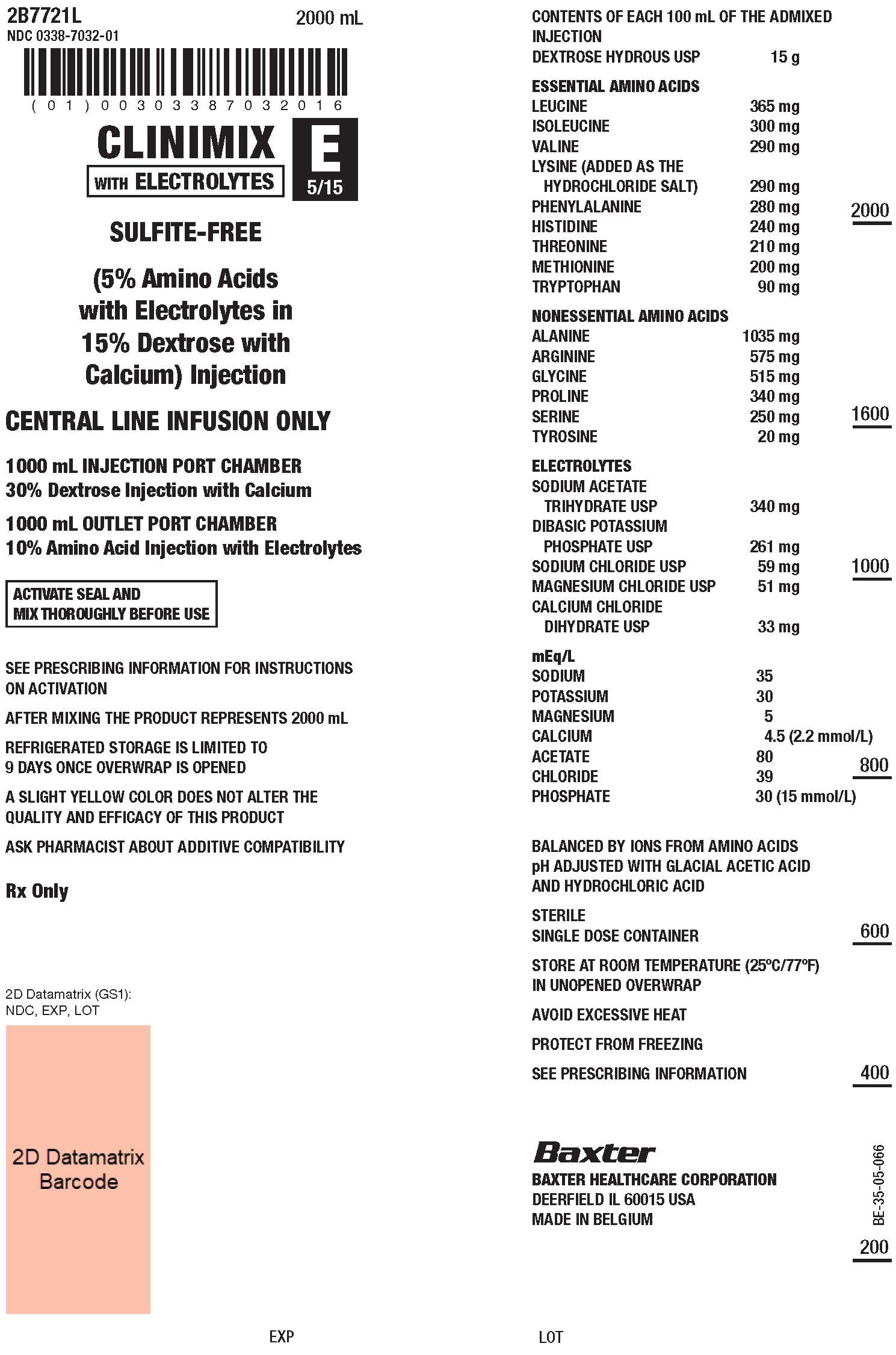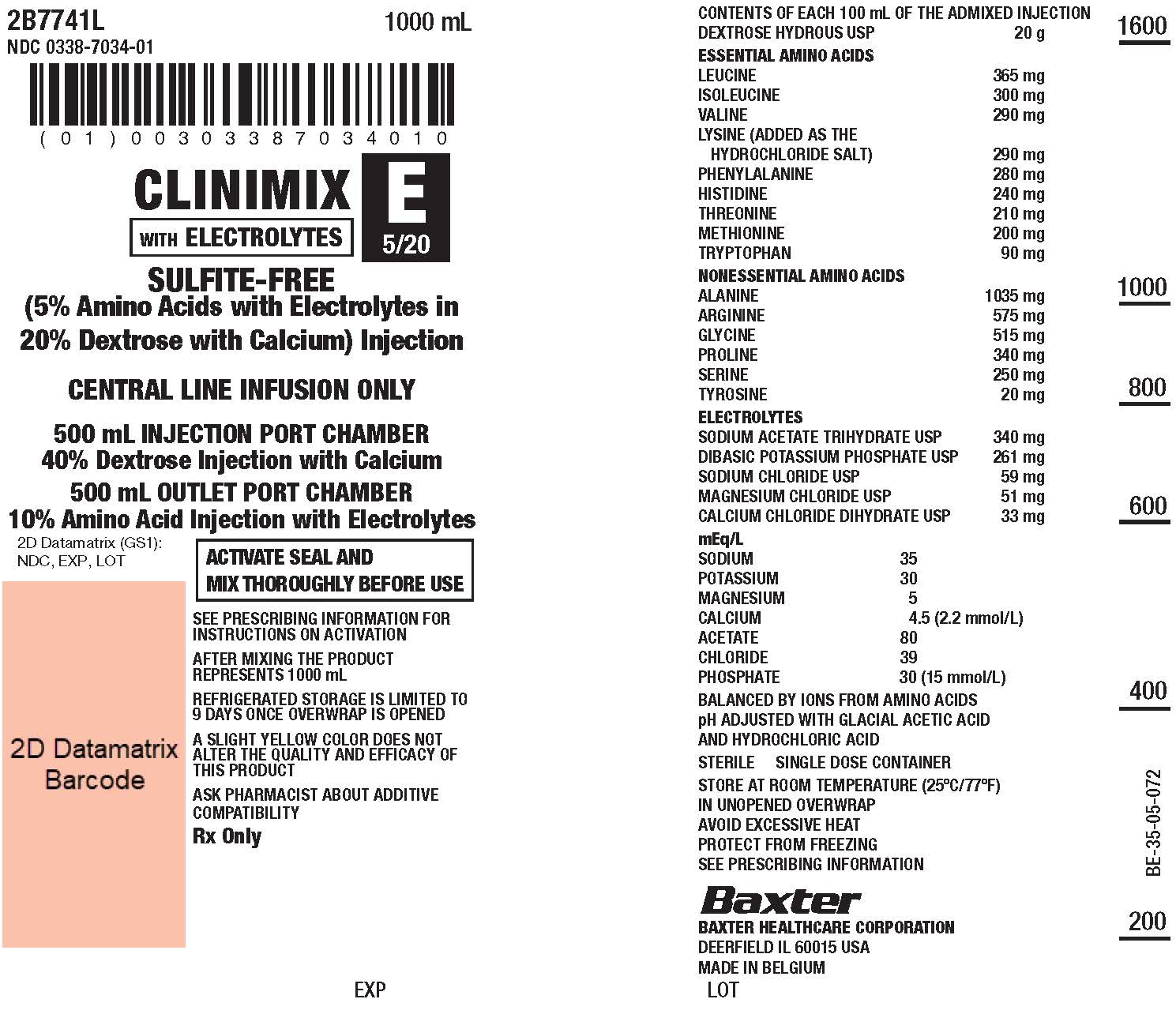 DRUG LABEL: CLINIMIX E
NDC: 0338-1142 | Form: INJECTION
Manufacturer: Baxter Healthcare Company
Category: prescription | Type: HUMAN PRESCRIPTION DRUG LABEL
Date: 20210413

ACTIVE INGREDIENTS: LEUCINE 201 mg/100 mL; PHENYLALANINE 154 mg/100 mL; LYSINE 159 mg/100 mL; METHIONINE 110 mg/100 mL; ISOLEUCINE 165 mg/100 mL; VALINE 160 mg/100 mL; HISTIDINE 132 mg/100 mL; THREONINE 116 mg/100 mL; TRYPTOPHAN 50 mg/100 mL; ALANINE 570 mg/100 mL; GLYCINE 283 mg/100 mL; ARGININE 316 mg/100 mL; PROLINE 187 mg/100 mL; SERINE 138 mg/100 mL; TYROSINE 11 mg/100 mL; SODIUM ACETATE 217 mg/100 mL; POTASSIUM PHOSPHATE, DIBASIC 261 mg/100 mL; MAGNESIUM CHLORIDE 51 mg/100 mL; SODIUM CHLORIDE 112 mg/100 mL; CALCIUM CHLORIDE 33 mg/100 mL; DEXTROSE 5 g/100 mL
INACTIVE INGREDIENTS: ACETIC ACID; WATER; NITROGEN

HIGHLIGHTS OF PRESCRIBING INFORMATION

These highlights do not include all the information needed to use CLINIMIX E safely and effectively. See full prescribing information for CLINIMIX E.
CLINIMIX E (amino acids with electrolytes in dextrose with calcium) injection, for intravenous use
Initial U.S. Approval: 1997

RECENT MAJOR CHANGES

Dosage and Administration, Instructions for Use (2.3, 2.7) 04/2021
  Warnings and Precautions (5.6) 04/2021
  Dosage and Administration (2.1, 2.3, 2.4, 2.6, 2.8) 09/2020

1 INDICATIONS AND USAGE

CLINIMIX E is indicated as a source of calories, protein, and electrolytes for patients requiring parenteral nutrition when oral or enteral nutrition is not possible, insufficient, or contraindicated. CLINIMIX E may be used to treat negative nitrogen balance in patients. (1)

2 DOSAGE AND ADMINISTRATION

See full prescribing information for information on preparation, administration, instructions for use, dosing considerations, including the recommended dosage in adults and pediatrics, and dosage modifications in patients with kidney disease. (2.1, 2.2, 2.3, 2.4, 2.5, 2.6, 2.7, 2.8)

3 DOSAGE FORMS AND STRENGTHS

CLINIMIX E injection is available in multiple strengths. See full prescribing information for detailed description of each formulation. (3, 11)

4 CONTRAINDICATIONS

- Concomitant treatment with ceftriaxone in neonates (28 days of age or younger). (4)
- Known hypersensitivity to one or more amino acids or dextrose. (4)
- Inborn errors of amino acid metabolism. (4)
- Patients with pulmonary edema or acidosis due to low cardiac output. (4)

5 WARNINGS AND PRECAUTIONS

- Pulmonary Embolism due to Pulmonary Vascular Precipitates: if signs of pulmonary distress occur, stop the infusion and initiate a medical evaluation. (5.1)
- Precipitation with Ceftriaxone: do not administer ceftriaxone simultaneously with CLINIMIX E via a Y-site. (4, 5.2, 8.4)
- Hypersensitivity Reactions: monitor for signs and symptoms and discontinue infusion if reactions occur. (5.3)
- Risk of Infections, Refeeding Complications, and Hyperglycemia or Hyperosmolar Hyperglycemic State: monitor for signs and symptoms; monitor laboratory parameters. (5.4, 5.5, 5.6)
- Vein Damage and Thrombosis: solutions with osmolarity of ≥ 900 mOsm/L must be infused through a central catheter. (2.2, 5.7)
- Hepatobiliary Disorders: monitor liver function parameters and ammonia levels. (5.8)
- Aluminum Toxicity: increased risk in patients with impaired kidney function, including preterm infants. (5.9, 8.4)
- Parenteral Nutrition Associated Liver Disease: increased risk in patients who receive parenteral nutrition for extended periods of time, especially preterm infants; monitor liver function tests, if abnormalities occur consider discontinuation or dosage reduction. (5.10, 8.4)
- Electrolyte Imbalance and Fluid Overload: patients with cardiac insufficiency or kidney disease may require adjustment of fluid, protein and electrolyte content. (5.11, 8.4)

6 ADVERSE REACTIONS

Adverse reactions include diuresis, extravasation, glycosuria, hyperglycemia, and hyperosmolar coma. (6)

To report SUSPECTED ADVERSE REACTIONS, contact Baxter Healthcare Corporation at 1-866-888-2472 or FDA at 1-800-FDA-1088 or www.fda.gov/medwatch

8 USE IN SPECIFIC POPULATIONS

Pediatric Use: increased risk of hypoglycemia/hyperglycemia: monitor serum glucose concentrations. (8.4)

FULL PRESCRIBING INFORMATION

1 INDICATIONS AND USAGE

CLINIMIX E is indicated as a source of calories, protein, and electrolytes for patients requiring parenteral nutrition when oral or enteral nutrition is not possible, insufficient, or contraindicated. CLINIMIX E may be used to treat negative nitrogen balance in patients.

2 DOSAGE AND ADMINISTRATION

2.1 Preparation Prior to Administration

- CLINIMIX E is available in a three port container configuration and a two port container configuration.
  - Three Port Container: the ports consist of one medication port, one additive port and one outlet port. Additives can be introduced to the container through the medication port and lipids through the additive port on the three port container.
  - Two Port Container: the ports consist of one medication port and one outlet port. Additives, including lipids, can be introduced to the container through the medication port on the two port container.
- Tear protective overwrap at slit and remove solution container. Small amounts of moisture may be found on the solution container from water permeating from inside the container. The amount of permeated water is insufficient to affect the solution significantly. If larger amounts of water are found, the container should be checked for tears or leaks.
- Inspect the container prior to activation. Some opacity of the plastic due to moisture absorption during the sterilization process may be observed. This is normal and does not affect the solution quality or safety. The opacity will diminish gradually. Evaluate the following:
  - If the outlet or additive port protectors are damaged, detached, or not present, discard container as solution path sterility may be impaired.
  - Check to ensure seal between chambers is intact, solutions are contained in separate chambers, and the content of the individual chambers is clear, colorless or slightly yellow. Discard if the seal is broken or if the solution is bright yellow or yellowish brown.
  - Check for minute leaks by separately squeezing each chamber. If external leaks or leakage between the chambers are found, discard solution as sterility or stability may be impaired.
- Lipids and/or additives can be introduced to the container after opening seal between chambers. Because additives may be incompatible, evaluate all additions to the plastic container for compatibility. Activate chambers of container prior to introduction of additives. Mix thoroughly when additives have been introduced. Supplemental medication may be added with a 19 to 22 gauge needle through the medication port.
- Calcium and phosphate ratios must be considered. Excess addition of calcium and phosphate, especially in the form of mineral salts, may result in the formation of calcium phosphate precipitates [see Warnings and Precautions (5.1)].
- Inspect the container to ensure precipitates have not formed during the mixing or addition of additives. A slight yellow color does not alter the quality and efficacy of this product. If lipid has been added, ensure the emulsion has not separated. Separation of the emulsion can be visibly identified by a yellowish streaking or the accumulation of yellowish droplets in the mixed emulsion. Discard the admixture if any of the above are observed.

2.2 Important Administration Instructions

- Set the vent to the closed position on a vented intravenous administration set to prevent air embolism.
- Use a dedicated line without any connections to avoid air embolism.
- CLINIMIX E is for intravenous infusion only into a central or peripheral vein. The choice of a central or peripheral venous route should depend on the osmolarity of the final infusate. Solutions with osmolarity of 900 mOsm/L or greater must be infused through a central catheter [see Warnings and Precautions (5.7)].
  - For central vein infusion only: CLINIMIX E 4.25/10, 5/15, 5/20, 8/10, 8/14
  - For central or peripheral vein infusion: CLINIMIX E 2.75/5 and 4.25/5
- The solution should be inspected for precipitates before admixing, after admixing, and again before administration.
- Use a 0.22 micron filter for administration of CLINIMIX E. If a lipid is also administered, use a 1.2 micron filter.
- If lipid emulsion is added, do not use administration sets and lines that contain di-2-ethylhexyl phthalate (DEHP). Administration sets that contain polyvinyl chloride (PVC) components have DEHP as a plasticizer.
- Ceftriaxone must not be administered simultaneously with calcium-containing intravenous solutions such as CLINIMIX E via a Y-site. However, in patients other than neonates, ceftriaxone and CLINIMIX E may be administered sequentially if the infusion lines are thoroughly flushed between infusions with a compatible fluid [see Contraindications (4), Warnings and Precautions (5.2)].

2.3 Instructions for Use

1. Open by tearing protective overwrap at slit and remove solution container. The two port container includes an oxygen-absorbing sachet. Discard the oxygen-absorbing sachet after removal from the overwrap.
2. To proceed with activation, the container should be at room temperature. Lay the room temperature container onto a flat surface. Grasp the container firmly on each side of the top of the container (Figure 1).
3. Starting from the top, using some pressure, slowly roll the container to open seal between chambers as shown in Figure 2. Do not pull or rip the seal apart. The seal must be completely opened towards the port side of the container. The upper section of the seal towards the hanger side can remain unbroken.
4. Mix the contents thoroughly by inverting the container upside down to ensure a homogenous admixture (Figure 3).
5. Once the container is mixed, check for leaks.
6. Make additions (if prescribed).
Because additives may be incompatible, evaluate all additions to the container for compatibility and stability of the resulting preparation. Consult with pharmacist, if available. Questions about compatibility may be directed to Baxter. If it is deemed advisable to introduce additives, use aseptic technique. For information on adding lipid emulsions see Dosage and Administration (2.4).
  a. Prepare medication port.
  b. Using syringe with 19 to 22 gauge needle, puncture resealable medication port and inject.
  c. Mix solution and medication thoroughly (Figure 3). For high density medication (high specific gravity), such as potassium chloride, squeeze ports while ports are upright and mix thoroughly.
7. Inspect final solution for discoloration and particulate matter. Check for leaks.
8. Spike and hang container.
  a. Suspend container from eyelet support.
  b. Twist off protector from outlet port at bottom of container (Figure 4).
  c. Attach administration set. Refer to complete directions accompanying set.
For single dose only. Discard unused portion.

Figures 1 – 4 (Three Port Container):

Figures 1 – 4 (Two Port Container):

Instructions on Storage

Storage After Removal of Overwrap:

Once removed from the protective overwrap, mixed (peel seal activated) or unmixed (peel seal intact), CLINIMIX E solutions may be stored under refrigeration for up to 9 days.

Storage Once any Additive is Added:

Use promptly after mixing. Any storage with additives should be under refrigeration and limited to a brief period of time, less than 24 hours. After removal from refrigeration, use promptly and complete the infusion within 24 hours. Any remaining mixture must be discarded.

Protect the activated parenteral nutrition solution from light.

2.4 Preparation and Addition of Lipid Emulsion

Three Port Container

1. Prior to adding lipid emulsion, mix amino acid and dextrose injection as shown in Figures 1-3.
2. Prepare lipid emulsion transfer set following instructions provided.
3. Attach transfer set to lipid emulsion container using aseptic technique.
4. Twist off protector on the additive port of the container.
5. Attach the transfer set to the exposed additive port.
6. Open clamp on transfer set.
7. After completing transfer, use appropriate plastic clamp or metal ferrule to seal off additive port tube.
8. Remove transfer set.
9. Mix contents of container thoroughly. Inspect final solution for discoloration and particulate matter. Check for leaks.

Two Port Container

1. Prior to adding lipid emulsion, mix amino acid and dextrose injection as shown in Figures 1-3.
2. Prepare lipid emulsion transfer set following instructions provided.
3. Attach transfer set to lipid emulsion container using aseptic technique.
4. Prepare medication port.
5. Using a 19 to 22 gauge needle, puncture resealable medication port.
6. Open clamp on transfer set and transfer lipid emulsion.
7. Remove needle.
8. Mix contents of container thoroughly. Inspect final solution for discoloration and particulate matter. Check for leaks.

Storage Once Lipids are Added:

Use promptly after mixing. Any storage with additives should be under refrigeration and limited to a brief period of time, no longer than 24 hours. After removal from refrigeration, use promptly and complete the infusion within 24 hours. Any mixture remaining must be discarded.

2.5 Dosing Considerations

- The dosage of CLINIMIX E should be individualized based on the patient’s clinical condition (ability to adequately metabolize amino acids and dextrose), body weight and nutritional/fluid requirements, as well as additional energy given orally/enterally to the patient. Prior to initiating CLINIMIX E the following patient information should be reviewed: all concomitant medications, gastrointestinal function and laboratory data such as electrolytes (including magnesium, calcium, and phosphorus), glucose, urea/creatinine, liver panel, complete blood count and triglyceride level (if adding lipid emulsion). Refer to the complete prescribing information of lipid emulsion for dosing information.
- CLINIMIX E formulations have varying concentrations of protein, carbohydrate and a standard concentration of electrolytes; thus infusion rates to achieve requirements will vary. Protein, caloric, fluid and electrolyte requirements all need to be taken into consideration when determining individual patient dosage needs.
- The dosage selection is based only on the recommended protein requirements. The maximum dextrose infusion rates and calorie and fluid requirements must also be considered when determining the clinically appropriate infusion rate for patients.
- CLINIMIX E meets the total nutritional requirements for protein and dextrose in stable patients, and can be individualized to meet specific needs with the addition of nutrients.
- Total daily fluid requirements can be met beyond the volume of amino acids solution by supplementing with non-carbohydrate or carbohydrate-containing electrolyte solutions. In many patients, provision of adequate calories in the form of hypertonic dextrose may require the administration of exogenous insulin to prevent hyperglycemia and glycosuria.
- Prior to administration of CLINIMIX E correct severe fluid, electrolyte and acid-base disorders.
- Monitor levels of serum potassium during therapy. It may be necessary to add additional potassium to the CLINIMIX E admixture.
- Lipid emulsion administration should be considered with prolonged use (more than 5 days) of CLINIMIX E in order to prevent essential fatty acid deficiency (EFAD). Serum lipids should be monitored for evidence of EFAD in patients maintained on fat-free parenteral nutrition. See prescribing information of lipid emulsion.
- The flow rate should be increased gradually. The flow rate must be adjusted taking into account the dose being administered, the daily volume intake, and the duration of the infusion.

2.6 Recommended Dosage in Adults

The recommended daily nutritional requirements for protein and dextrose compared to the amount of nutrition provided by CLINIMIX E are shown in Table 1.
As indicated on an individual basis, maintenance vitamins, additional electrolytes, trace elements and other components (including lipids) should be administered as required to prevent deficiencies and complications from developing.
The maximum infusion rates in adult patients are show in Table 2.

In addition to meeting protein needs, the administration rate should be governed, especially during the first few day of therapy, by the patient’s tolerance to dextrose. Daily intake of amino acids and dextrose should be increased gradually to the maximum required dose as indicated by frequent determinations of blood glucose levels.

Table 1: Nutritional Comparison – Adult Patients
 | Recommended CLINIMIX E Adult Dosage
 | CLINIMIX E 2.75/5 | CLINIMIX E 4.25/5 | CLINIMIX E 4.25/10 | CLINIMIX E 5/15 | CLINIMIX E 5/20 | CLINIMIX E 8/10 | CLINIMIX E 8/14
Fluid (mL/kg/day) | 29 to 40 | 19 to 40 | 19 to 40 | 16 to 40 | 16 to 40 | 10 to 25 | 10 to 25
Protein [Protein is provided as amino acids. When infused intravenously amino acids are metabolized and utilized as the building blocks of protein.] (g/kg/day) (Nitrogen g/kg/day) | 0.8 to 1.1 (0.13 to 0.18) | 0.8 to 1.7 (0.13 to 0.27) | 0.8 to 1.7 (0.13 to 0.27) | 0.8 to 2 (0.13 to 0.32) | 0.8 to 2 (0.13 to 0.32) | 0.8 to 2 (0.13 to 0.32) | 0.8 to 2 (0.13 to 0.32)
Dextrose (g/kg/day) | 1.45 to 2 | 0.95 to 2 | 1.9 to 4 | 2.4 to 6 | 3.2 to 8 | 1 to 2.5 | 1.4 to 3.5

Table 2: Maximum Infusion Rate in Adult Patients
 |  | Maximum Infusion Rates in Adults Patients
 |  | CLINIMIX E 2.75/5 | CLINIMIX E 4.25/5 | CLINIMIX E 4.25/10 | CLINIMIX E 5/15 | CLINIMIX E 5/20 | CLINIMIX E 8/10 | CLINIMIX E 8/14
Maximum Infusion Rate (mL/kg/hour) |  | 3.6 | 2.4 | 2.4 | 1.67 | 1.25 | 1.3 | 1.3
Corresponding infusion rate | Amino Acid (g/kg/hour) | 0.1 [Rate limiting factor] | 0.1 | 0.1 | 0.08 | 0.06 | 0.1 | 0.1
Corresponding infusion rate | Dextrose (g/kg/hour) | 0.18 | 0.12 | 0.24 | 0.25 | 0.25 | 0.13 | 0.18

2.7 Dosage Modifications in Patients with Kidney Disease

Prior to administration, correct severe fluid or electrolyte imbalances. Closely monitor serum electrolyte levels and adjust the volume of CLINIMIX E administered as required [see Warnings and Precautions (5.11)].

Chronic kidney disease patients with less than nephrotic range proteinuria require 0.8 g of protein/kg/day. Chronic kidney disease patients with nephrotic range proteinuria require 0.8 g of protein/kg/day plus 1 g of protein for each gram of proteinuria. Patients needing dialysis should receive from 1.2 g of protein/kg/day up to a maximum of 2.5 g of protein/kg/day depending on the nutritional status and the dialysis modality. Serum electrolyte levels should be closely monitored. The CLINIMIX E dosage can be adjusted based on the severity of kidney disease, supplementing protein as indicated. If required, additional amino acids may be added to the CLINIMIX E container or infused separately. Compatibility of additions should be evaluated by a pharmacist and questions may be directed to Baxter.

2.8 Recommended Dosage in Pediatric Patients

The dosage and constant infusion rate of intravenous dextrose must be selected with caution in pediatric patients, particularly neonates and low weight infants, because of the increased risk of hyperglycemia/hypoglycemia [see Use in Specific Populations (8.4)]. Frequent monitoring of serum glucose concentrations is required when dextrose is prescribed to pediatric patients, particularly neonates and low birth weight infants. The infusion rate and volume should be determined by the consulting physician experienced in pediatric intravenous fluid therapy.

In pediatric patients, CLINIMIX E is dosed on the basis of protein provided as amino acids. The recommended dosage, by age group is provided in Tables 3 - 6. Infusion rates are based on protein and do not take carbohydrates, fluid or electrolytes into consideration.

This product does not contain the amino acids cysteine and taurine, considered conditionally essential for neonates and infants. If possible, these amino acids should be added to this product if used in this pediatric population.

Table 3: Preterm and Term Infants Less than 1 Month of Age
 | Recommended CLINIMIX E Dosage in Preterm and Term Infants Less than 1 Month of Age
 | CLINIMIX E 2.75/5 | CLINIMIX E 4.25/5 | CLINIMIX E 4.25/10 | CLINIMIX E 5/15 | CLINIMIX E 5/20 | CLINIMIX E 8/10 | CLINIMIX E 8/14
Infusion Rate Range (mL/kg/hr) | 4.5 to 6 | 2.9 to 3.9 | 2.9 to 3.9 | 2.5 to 3.3 | 2.5 to 3.3 | 1.6 to 2.1 | 1.6 to 2.1
Fluid (mL/kg/day) | 108 to 144 | 70 to 94 | 70 to 94 | 60 to 79 | 60 to 79 | 38.4 to 50 | 38.4 to 50
Protein [Protein is provided as amino acids. When infused intravenously amino acids are metabolized and utilized as the building blocks of protein.] (g/kg/day) (Nitrogen g/kg/day) | 3 to 4 (0.48 to 0.64) | 3 to 4 (0.48 to 0.64) | 3 to 4 (0.48 to 0.64) | 3 to 4 (0.48 to 0.64) | 3 to 4 (0.48 to 0.64) | 3 to 4 (0.48 to 0.64) | 3 to 4 (0.48 to 0.64)
Dextrose (g/kg/day) | 5.4 to 7.2 | 3.5 to 4.7 | 7 to 9.4 | 9 to 11.9 | 12 to 15.8 | 3.8 to 5 | 5.4 to 7

Table 4: Pediatric Patients 1 Month to Less than 1 Year of Age
 | Recommended CLINIMIX E Dosage in Pediatric Patients 1 Month to Less than 1 Year of Age
 | CLINIMIX E 2.75/5 | CLINIMIX E 4.25/5 | CLINIMIX E 4.25/10 | CLINIMIX E 5/15 | CLINIMIX E 5/20 | CLINIMIX E 8/10 | CLINIMIX E 8/14
Infusion Rate Range (mL/kg/hr) | 3 to 4.5 | 2 to 2.9 | 2 to 2.9 | 1.7 to 2.5 | 1.7 to 2.5 | 1 to 1.6 | 1 to 1.6
Fluid (mL/kg/day) | 72 to 108 | 48 to 70 | 48 to 70 | 41 to 60 | 41 to 60 | 24 to 38.4 | 24 to 38.4
Protein [Protein is provided as amino acids. When infused intravenously amino acids are metabolized and utilized as the building blocks of protein.] (g/kg/day) (Nitrogen g/kg/day) | 2 to 3 (0.32 to 0.48) | 2 to 3 (0.32 to 0.48) | 2 to 3 (0.32 to 0.48) | 2 to 3 (0.32 to 0.48) | 2 to 3 (0.32 to 0.48) | 2 to 3 (0.32 to 0.48) | 2 to 3 (0.32 to 0.48)
Dextrose (g/kg/day) | 3.6 to 5.4 | 2.4 to 3.5 | 4.8 to 7 | 6.1 to 9 | 8.2 to 12 | 2.4 to 3.8 | 3.4 to 5.4

Table 5: Pediatric Patients 1 Year to Less than 11 Years of Age
 | Recommended CLINIMIX E Dosage in Pediatric Patients 1 Year to Less than 11 Years of Age
 | CLINIMIX E 2.75/5 | CLINIMIX E 4.25/5 | CLINIMIX E 4.25/10 | CLINIMIX E 5/15 | CLINIMIX E 5/20 | CLINIMIX E 8/10 | CLINIMIX E 8/14
Infusion Rate Range (mL/kg/hr) | 1.5 to 3 | 1 to 2 | 1 to 2 | 0.8 to 1.7 | 0.8 to 1.7 | 0.5 to 1 | 0.5 to 1
Fluid (mL/kg/day) | 36 to 72 | 24 to 48 | 24 to 48 | 19 to 41 | 19 to 41 | 12 to 24 | 12 to 24
Protein [Protein is provided as amino acids. When infused intravenously amino acids are metabolized and utilized as the building blocks of protein.] (g/kg/day) (Nitrogen g/kg/day) | 1 to 2 (0.16 to 0.32) | 1 to 2 (0.16 to 0.32) | 1 to 2 (0.16 to 0.32) | 1 to 2 (0.16 to 0.32) | 1 to 2 (0.16 to 0.32) | 1 to 2 (0.16 to 0.32) | 1 to 2 (0.16 to 0.32)
Dextrose (g/kg/day) | 1.8 to 3.6 | 1.2 to 2.4 | 2.4 to 4.8 | 2.9 to 6.1 | 3.8 to 8.2 | 1.2 to 2.4 | 1.7 to 3.4

Table 6: Pediatric Patients 11 Years to 17 Years of Age
 | Recommended CLINIMIX E Dosage in Pediatric Patients 11 Years to 17 Years of Age
 | CLINIMIX E 2.75/5 | CLINIMIX E 4.25/5 | CLINIMIX E 4.25/10 | CLINIMIX E 5/15 | CLINIMIX E 5/20 | CLINIMIX E 8/10 | CLINIMIX E 8/14
Infusion Rate Range (mL/kg/hr) | 1.2 to 2.3 | 0.8 to 1.5 | 0.8 to 1.5 | 0.7 to 1.3 | 0.7 to 1.3 | 0.4 to 0.8 | 0.4 to 0.8
Fluid (mL/kg/day) | 29 to 55 | 19 to 36 | 19 to 36 | 17 to 31 | 17 to 31 | 9.6 to 19.2 | 9.6 to 19.2
Protein [Protein is provided as amino acids. When infused intravenously amino acids are metabolized and utilized as the building blocks of protein.] (g/kg/day) (Nitrogen g/kg/day) | 0.8 to 1.5 (0.13 to 0.24) | 0.8 to 1.5 (0.13 to 0.24) | 0.8 to 1.5 (0.13 to 0.24) | 0.8 to 1.5 (0.13 to 0.24) | 0.8 to 1.5 (0.13 to 0.24) | 0.8 to 1.5 (0.13 to 0.24) | 0.8 to 1.5 (0.13 to 0.24)
Dextrose (g/kg/day) | 1.4 to 2.8 | 1 to 1.8 | 1.9 to 3.6 | 2.5 to 4.7 | 3.4 to 6.2 | 1 to 1.9 | 1.4 to 2.7

2.9 Discontinuation of CLINIMIX E injection

To reduce the risk of hypoglycemia after discontinuation, a gradual decrease in flow rate in the last hour of infusion should be considered.

3 DOSAGE FORMS AND STRENGTHS

CLINIMIX E injection is available in 1000 mL and 2000 mL dual chamber containers. The individual chambers contain essential and nonessential amino acids with electrolytes and dextrose with calcium. Table 7 describes the individual components of CLINIMIX E.

Table 7: INGREDIENTS PER 100mL OF CLINIMIX E
Strength of CLINIMIX E |  | CLINIMIX E 2.75/5 sulfite‑free (2.75% Amino Acid in 5% Dextrose) Injection | CLINIMIX E 4.25/5 sulfite‑free (4.25% Amino Acid in 5% Dextrose) Injection | CLINIMIX E 4.25/10 sulfite‑free (4.25% Amino Acid in 10% Dextrose) Injection | CLINIMIX E 5/15 sulfite‑free (5% Amino Acid in 15% Dextrose) Injection | CLINIMIX 5/20 sulfite‑free (5% Amino Acid in 20% Dextrose) Injection | CLINIMIX E 8/10 sulfite‑free (8% Amino Acid in 10% Dextrose) Injection | CLINIMIX E 8/14 sulfite‑free (8% Amino Acid in 14% Dextrose) Injection
 | Dextrose Hydrous, USP (g/100 mL) | 5 | 5 | 10 | 15 | 20 | 10 | 14
 | Amino Acids (g/100 mL) | 2.75 | 4.25 | 4.25 | 5 | 5 | 8 | 8
 | Total Nitrogen (mg/100 mL) | 454 | 702 | 702 | 826 | 826 | 1320 | 1320
Essential Amino Acids (mg/100 mL) | Leucine | 201 | 311 | 311 | 365 | 365 | 584 | 584
Essential Amino Acids (mg/100 mL) | Isoleucine | 165 | 255 | 255 | 300 | 300 | 480 | 480
Essential Amino Acids (mg/100 mL) | Valine | 160 | 247 | 247 | 290 | 290 | 464 | 464
Essential Amino Acids (mg/100 mL) | Lysine (added as the hydrochloride salt) | 159 | 247 | 247 | 290 | 290 | 464 | 464
Essential Amino Acids (mg/100 mL) | Phenylalanine | 154 | 238 | 238 | 280 | 280 | 448 | 448
Essential Amino Acids (mg/100 mL) | Histidine | 132 | 204 | 204 | 240 | 240 | 384 | 384
Essential Amino Acids (mg/100 mL) | Threonine | 116 | 179 | 179 | 210 | 210 | 336 | 336
Essential Amino Acids (mg/100 mL) | Methionine | 110 | 170 | 170 | 200 | 200 | 320 | 320
Essential Amino Acids (mg/100 mL) | Tryptophan | 50 | 77 | 77 | 90 | 90 | 144 | 144
Nonessential Amino Acids (mg/100 mL) | Alanine | 570 | 880 | 880 | 1035 | 1035 | 1656 | 1656
Nonessential Amino Acids (mg/100 mL) | Arginine | 316 | 489 | 489 | 575 | 575 | 920 | 920
Nonessential Amino Acids (mg/100 mL) | Glycine | 283 | 438 | 438 | 515 | 515 | 824 | 824
Nonessential Amino Acids (mg/100 mL) | Proline | 187 | 289 | 289 | 340 | 340 | 544 | 544
Nonessential Amino Acids (mg/100 mL) | Serine | 138 | 213 | 213 | 250 | 250 | 400 | 400
Nonessential Amino Acids (mg/100 mL) | Tyrosine | 11 | 17 | 17 | 20 | 20 | 32 | 32
Electrolytes (mg/100 mL) | Sodium Acetate Trihydrate, USP | 217 | 297 | 297 | 340 | 340 | 0 | 0
Electrolytes (mg/100 mL) | Dibasic Potassium Phosphate, USP | 261 | 261 | 261 | 261 | 261 | 261 | 261
Electrolytes (mg/100 mL) | Sodium Chloride, USP | 112 | 77 | 77 | 59 | 59 | 205 | 205
Electrolytes (mg/100 mL) | Magnesium Chloride, USP | 51 | 51 | 51 | 51 | 51 | 51 | 51
Electrolytes (mg/100 mL) | Calcium Chloride Dihydrate, USP | 33 | 33 | 33 | 33 | 33 | 33 | 33
Electrolyte Profile (mEq/L) [Balanced by ions from amino acids.] | Sodium | 35 | 35 | 35 | 35 | 35 | 35 | 35
Electrolyte Profile (mEq/L) [Balanced by ions from amino acids.] | Potassium | 30 | 30 | 30 | 30 | 30 | 30 | 30
Electrolyte Profile (mEq/L) [Balanced by ions from amino acids.] | Magnesium | 5 | 5 | 5 | 5 | 5 | 5 | 5
Electrolyte Profile (mEq/L) [Balanced by ions from amino acids.] | Calcium | 4.5 (2.2 mmol/L) | 4.5 (2.2 mmol/L) | 4.5 (2.2 mmol/L) | 4.5 (2.2 mmol/L) | 4.5 (2.2 mmol/L) | 4.5 (2.2 mmol/L) | 4.5 (2.2 mmol/L)
Electrolyte Profile (mEq/L) [Balanced by ions from amino acids.] | Acetate [Derived from glacial acetic acid (for pH adjustment) and sodium acetate.] | 51 | 70 | 70 | 80 | 80 | 83 | 83
Electrolyte Profile (mEq/L) [Balanced by ions from amino acids.] | Chloride [Contributed by calcium chloride, lysine hydrochloride, magnesium chloride, sodium chloride, and hydrochloric acid.] | 39 | 39 | 39 | 39 | 39 | 76 | 76
Electrolyte Profile (mEq/L) [Balanced by ions from amino acids.] | Phosphate (as HPO4=) | 30 (15 mmol/L) | 30 (15 mmol/L) | 30 (15 mmol/L) | 30 (15 mmol/L) | 30 (15 mmol/L) | 30 (15 mmol/L) | 30 (15 mmol/L)
 | pH [pH of sulfite-free amino acid injection with electrolytes in the outlet port chamber was adjusted with glacial acetic acid and pH of dextrose injection port chamber was adjusted with hydrochloric acid.] (Range) | 6.0 (4.5 to 7.0) | 6.0 (4.5 to 7.0) | 6.0 (4.5 to 7.0) | 6.0 (4.5 to 7.0) | 6.0 (4.5 to 7.0) | 6.0 (4.5 to 7.0) | 6.0 (4.5 to 7.0)
 | Osmolarity (mOsmol/L) (calc) | 665 | 815 | 1070 | 1395 | 1650 | 1450 | 1650
Caloric Content (kcal/L) | From Dextrose | 170 | 170 | 340 | 510 | 680 | 343 | 477
Caloric Content (kcal/L) | From Amino Acids | 110 | 170 | 170 | 200 | 200 | 320 | 320
Caloric Content (kcal/L) | TOTAL (Dextrose and Amino Acids) | 280 | 340 | 510 | 710 | 880 | 663 | 797

4 CONTRAINDICATIONS

The use of CLINIMIX E is contraindicated in:
1. Neonates (28 days of age or younger) receiving concomitant treatment with ceftriaxone, even if separate infusion lines are used, due to the risk of fatal ceftriaxone calcium salt precipitation in the neonate’s bloodstream [see Warnings and Precautions (5.2), Use in Specific Populations (8.4)].
2. Patients with known hypersensitivity to one or more amino acids or dextrose [see Warnings and Precautions (5.3)].
3. Patients with inborn errors of amino acid metabolism due to risk of severe metabolic and neurologic complications.
4. Patients with pulmonary edema or acidosis due to low cardiac output.

5 WARNINGS AND PRECAUTIONS

5.1 Pulmonary Embolism due to Pulmonary Vascular Precipitates

Pulmonary vascular precipitates causing pulmonary vascular emboli and pulmonary distress have been reported in patients receiving parenteral nutrition. In some cases, fatal outcomes due to pulmonary embolism have occurred. Patients, especially those with hypophosphatemia, may require the addition of phosphate. To prevent hypocalcemia, calcium supplementation should always accompany phosphate administration. Excessive addition of calcium and phosphate increases the risk of the formation of calcium phosphate precipitates. Precipitates have been reported even in the absence of phosphate salt in the solution. Precipitation following passage through an in-line filter and suspected in vivo precipitate formation has also been reported. If signs of pulmonary distress occur, stop the infusion and initiate a medical evaluation. In addition to inspection of the solution [see Dosage and Administration (2.1, 2.2, 2.3, 2.4)], the infusion set and catheter should also periodically be checked for precipitates.

5.2 Precipitation with Ceftriaxone

Precipitation of ceftriaxone-calcium can occur when ceftriaxone is mixed with calcium-containing parenteral nutrition solutions, such as CLINIMIX E, in the same intravenous administration line. Do not administer ceftriaxone simultaneously with CLINIMIX E via a Y-site.

Deaths have occurred in neonates (less than 28 days of age) who received concomitant intravenous calcium-containing solutions with ceftriaxone resulting from calcium-ceftriaxone precipitates in the lungs and kidneys, even when separate infusion lines were used. CLINIMIX E is contraindicated in neonates receiving ceftriaxone [see Contraindications (4),Use in Specific Populations (8.4)].

In patients older than 28 days (including adults), ceftriaxone and CLINIMIX E may be administered sequentially if the infusion lines are thoroughly flushed between infusions with a compatible fluid.

5.3 Hypersensitivity Reactions

Hypersensitivity/infusion reactions including anaphylaxis have been reported with CLINIMIX E. Stop infusion immediately and treat patient accordingly if any signs or symptoms of a hypersensitivity reaction develop. Signs or symptoms may include: hypotension, hypertension, peripheral cyanosis, tachycardia, dyspnea, vomiting, nausea, urticaria, rash, pruritus, erythema, hyperhidrosis, pyrexia, and chills.

5.4 Risk of Infections

Patients who require parenteral nutrition are at high risk of infections because the nutritional components of these solutions can support microbial growth. Infection and sepsis may also occur as a result of the use of intravenous catheters to administer parenteral nutrition.

The risk of infection is increased in patients with malnutrition-associated immunosuppression, hyperglycemia exacerbated by dextrose infusion, long-term use and poor maintenance of intravenous catheters, or immunosuppressive effects of other concomitant conditions, drugs, or other components of the parenteral formulation (e.g., lipid emulsion).

To decrease the risk of infection, ensure aseptic technique in catheter placement and maintenance, as well as aseptic technique in the preparation and administration of the nutritional formula.

Monitor for signs and symptoms (including fever and chills) of early infections, including laboratory test results (including leukocytosis and hyperglycemia) and frequent checks of the parenteral access device and insertion site for edema, redness and discharge.

5.5 Refeeding Syndrome

Refeeding severely undernourished patients may result in refeeding syndrome, characterized by the intracellular shift of potassium, phosphorus, and magnesium as the patient becomes anabolic. Thiamine deficiency and fluid retention may also develop. To prevent these complications, monitor severely undernourished patients and slowly increase nutrient intakes.

5.6 Hyperglycemia or Hyperosmolar Hyperglycemic State

When using CLINIMIX E in patients with diabetes mellitus, impaired glucose tolerance may worsen hyperglycemia. Administration of dextrose at a rate exceeding the patient’s utilization rate may lead to hyperglycemia, coma, and death. Patients with dehydration, resulting in a transient reduction in glomerular filtration rate and pre-renal azotemia, may be at greater risk of developing hyperosmolar hyperglycemic state. Monitor blood glucose levels and treat hyperglycemia to maintain optimum levels while administering CLINIMIX E. Insulin may be administered or adjusted to maintain optimal blood glucose levels during CLINIMIX E administration.

5.7 Vein Damage and Thrombosis

Solutions with osmolarity of 900 mOsm/L or greater must be infused through a central catheter. CLINIMIX E solutions containing more than 5% dextrose have an osmolarity greater than or equal to 900 mOsm/L. CLINIMIX E 4.25/10, 5/15, 5/20, 8/10 and 8/14 are indicated for administration into a central vein only, such as the superior vena cava [see Dosage and Administration (2.2)]. The infusion of hypertonic nutrient injections into a peripheral vein may result in vein irritation, vein damage, and/or thrombosis.

CLINIMIX E 2.75/5 and 4.25/5 are indicated for peripheral administration, or may be infused into a central vein [see Dosage and Administration (2.2)]. The primary complication of peripheral access is venous thrombophlebitis, which manifests as pain, erythema, tenderness or a palpable cord. Remove the catheter as soon as possible, if thrombophlebitis develops.

5.8 Hepatobiliary Disorders

Hepatobiliary disorders are known to develop in some patients without preexisting liver disease who receive parenteral nutrition, including cholecystitis, cholelithiasis, cholestasis, hepatic steatosis, fibrosis and cirrhosis, possibly leading to hepatic failure. The etiology of these disorders is thought to be multifactorial and may differ between patients.

Increase in blood ammonia levels and hyperammonemia may occur in patients receiving amino acid solutions. In some patients this may indicate hepatic insufficiency or the presence of an inborn error of amino acid metabolism [see Contraindications (4)].

Monitor liver function parameters and ammonia levels. Patients developing signs of hepatobiliary disorders should be assessed early by a clinician knowledgeable in liver diseases in order to identify possible causative and contributory factors, and possible therapeutic and prophylactic interventions.

5.9 Aluminum Toxicity

CLINIMIX E contains no more than 25 mcg/L of aluminum. The aluminum contained in CLINIMIX E may reach toxic levels with prolonged administration in patients with impaired kidney function.

Preterm infants are at greater risk because their kidneys are immature, and they require large amounts of calcium and phosphate solutions, which contain aluminum. Patients with impaired kidney function, including preterm infants, who receive parenteral levels of aluminum at greater than 4 to 5 mcg/kg/day, accumulate aluminum at levels associated with central nervous system and bone toxicity. Tissue loading may occur at even lower rates of administration.

5.10 Risk of Parenteral Nutrition Associated Liver Disease

Parenteral Nutrition Associated Liver Disease (PNALD) has been reported in patients who receive parenteral nutrition for extended periods of time, especially preterm infants, and can present as cholestasis or steatohepatitis. The exact etiology is unknown and is likely multifactorial. If CLINIMIX E treated patients develop liver test abnormalities consider discontinuation or dosage reduction.

5.11 Electrolyte Imbalance and Fluid Overload

Patients with abnormal renal function due to pre-renal azotemia, renal obstruction, or intrinsic kidney disease may be at increased risk of electrolyte and fluid volume imbalance. Patients with cardiac insufficiency due to left ventricular systolic dysfunction are susceptible to excess fluid accumulation. Use CLINIMIX E with caution in patients with cardiac insufficiency or kidney disease. CLINIMIX E dosage may require adjustment with specific attention to fluid, protein, and electrolyte content in these patients.

Monitor renal function parameters. Patients developing signs of kidney disease should be assessed early by a clinician knowledgeable in kidney disease in order to determine the appropriate CLINIMIX E dosage and other treatment options.

5.12 Monitoring/Laboratory Tests

Monitor fluid and electrolyte status, serum osmolarity, blood glucose, liver and kidney function, blood count and coagulation parameters throughout treatment. In situations of severely elevated electrolyte levels, stop CLINIMIX E until levels have been corrected.

6 ADVERSE REACTIONS

The following serious adverse reactions are discussed in greater detail in other sections of the prescribing information.

- Pulmonary embolism due to pulmonary vascular precipitates [see Warnings and Precautions (5.1)]
- Death in neonates due to calcium-ceftriaxone precipitates [see Warnings and Precautions (5.2)]
- Hypersensitivity reactions [see Warnings and Precautions (5.3)]
- Risk of Infections [see Warnings and Precautions (5.4)]
- Refeeding syndrome [see Warnings and Precautions (5.5)]
- Hyperglycemia or hyperosmolar hyperglycemic state [see Warnings and Precautions (5.6)]
- Vein damage and thrombosis [see Warnings and Precautions (5.7)]
- Hepatobiliary disorders [see Warnings and Precautions (5.8)]
- Parenteral Nutrition Associated Liver Disease (PNALD) [see Warnings and Precautions (5.10)]
- Electrolyte imbalance and fluid overload [see Warnings and Precautions (5.11)]

The following adverse reactions from voluntary reports or clinical studies have been reported with CLINIMIX E. Because many of these reactions were reported voluntarily from a population of uncertain size, it is not always possible to reliably estimate their frequency or establish a causal relationship to drug exposure.

- Diuresis
- Extravasation
- Glycosuria
- Hyperglycemia
- Hyperosmolar coma

7 DRUG INTERACTIONS

7.1 Drugs that Can Cause Hyperkalemia

Because of its potassium content, CLINIMIX E should be administered with caution in patients treated with agents or products that can cause hyperkalemia or increase the risk of hyperkalemia, such as potassium sparing diuretics (amiloride, spironolactone, triamterene), with ACE inhibitors, angiotensin II receptor antagonists, or the immunosuppressants tacrolimus and cyclosporine.

8 USE IN SPECIFIC POPULATIONS

8.1 Pregnancy

Risk Summary

There are no adequate or well-controlled studies in pregnant women with CLINIMIX E. Additionally, animal reproduction studies have not been conducted with amino acids and electrolytes and dextrose. It is not known whether CLINIMIX E can cause fetal harm when administered to a pregnant woman.

The estimated background risk of major birth defects and miscarriage for the indicated population is unknown. However, the estimated background risk in the U.S. general population of major birth defects is 2 to 4% and of miscarriage is 15 to 20% of clinically recognized pregnancies.

Clinical Considerations

Disease-Associated Maternal and/or Embryo-Fetal Risk

Based on clinical practice guidelines, parenteral nutrition should be considered in cases of severe maternal malnutrition where nutritional requirements cannot be fulfilled by the enteral route because of the risks to the fetus associated with severe malnutrition, such as preterm delivery, low birth weight, intrauterine growth restriction, congenital malformations and perinatal mortality.

8.2 Lactation

Risk Summary

It is not known whether CLINIMIX E is present in human milk. There are no data on the effects of CLINIMIX E on the breastfed infant or on milk production. The developmental and health benefits of breastfeeding should be considered along with the mother’s clinical need for CLINIMIX E and any potential adverse effects on the breastfed child from CLINIMIX E or from the underlying maternal condition.

8.4 Pediatric Use

Safety and effectiveness of CLINIMIX E in pediatric patients have not been established by adequate and well-controlled studies. Use of dextrose, amino acid infusions and electrolytes in pediatric patients is based on clinical practice [see Dosage and Administration (2.8)].

Deaths have occurred in neonates (28 days of age or younger) who received concomitant intravenous calcium-containing solutions with ceftriaxone resulting from calcium-ceftriaxone precipitates in the lungs and kidneys, even when separate infusion lines were used. CLINIMIX E is contraindicated in neonates receiving ceftriaxone [see Contraindications (4), Warnings and Precautions (5.2)].

Newborns, especially those born premature and with low birth weight, are at increased risk of developing hypo – or hyperglycemia and therefore need close monitoring during treatment with intravenous glucose solutions to ensure adequate glycemic control in order to avoid potential long term adverse effects. Hypoglycemia in the newborn can cause prolonged seizures, coma and brain damage. Hyperglycemia has been associated with intraventricular hemorrhage, late onset bacterial and fungal infection, retinopathy of prematurity, necrotizing enterocolitis, bronchopulmonary dysplasia, prolonged length of hospital stay, and death. Plasma electrolyte concentrations should be closely monitored in the pediatric population as this population may have impaired ability to regulate fluids and electrolytes.

Because of immature renal function, preterm infants receiving prolonged treatment with CLINIMIX E, may be at risk of aluminum toxicity [see Warnings and Precautions (5.9)].

Patients, including pediatric patients, may be at risk for Parenteral Nutrition Associated Liver Disease (PNALD) [see Warnings and Precautions (5.10)].

Hyperammonemia is of special significance in infants (birth to two years). This reaction appears to be related to a deficiency of the urea cycle amino acids of genetic or product origin. It is essential that blood ammonia be measured frequently in infants [see Warnings and Precautions (5.8)].

8.5 Geriatric Use

Clinical studies of CLINIMIX E did not include sufficient numbers of subjects aged 65 and over to determine whether they respond differently from other younger subjects. Other reported clinical experience has not identified differences in responses between the elderly and younger patients.

In general, dose selection for an elderly patient should be cautious, usually starting at the low end of the dosing range, reflecting the greater frequency of decreased hepatic, renal, or cardiac function, and of concomitant disease or drug therapy.

10 OVERDOSAGE

An increased infusion rate of CLINIMIX E can cause hyperglycemia, hyperosmolality, and adverse effects on water and electrolyte balance [see Warnings and Precautions (5.6, 5.11)].

Severe hyperglycemia and severe dilutional hyponatremia, and their complications, can be fatal.

Discontinue infusion and institute appropriate corrective measures in the event of overhydration or solute overload during therapy, with particular attention to respiratory and cardiovascular systems.

For current information on the management of poisoning or overdosage, contact the National Poison Control Center at 1-800-222-1222 or www.poison.org.

11 DESCRIPTION

CLINIMIX E sulfite-free (amino acids with electrolytes in dextrose with calcium) injection for intravenous use consists of sterile, nonpyrogenic, hypertonic solutions in a dual chamber container.

The outlet port chamber contains essential and nonessential amino acids with electrolytes. The formulas for the individual electrolytes and amino acids are provided in Table 8.

Table 8: Formulas for Electrolytes and Amino Acids
Electrolytes
Sodium Acetate | C2H3NaO2•3H2O
Potassium Phosphate, dibasic | K2HPO4
Magnesium Chloride | MgCl2•6H2O
Sodium Chloride | NaCl
Essential Amino Acids
Leucine | (CH3)2 CHCH2CH (NH2) COOH
Isoleucine | CH3CH2CH (CH3) CH (NH2) COOH
Valine | (CH3)2 CHCH (NH2) COOH
Lysine (added as the hydrochloride salt) | H2N (CH2)4 CH (NH2) COOH
Phenylalanine | (C6H5) CH2 CH (NH2) COOH
Histidine | (C3H3N2) CH2CH (NH2) COOH
Threonine | CH3CH (OH) CH (NH2) COO
Methionine | CH3S (CH2)2 CH (NH2) COOH
Tryptophan | (C8H6N) CH2 CH (NH2) COOH
Nonessential Amino Acids
Alanine | CH3CH (NH2) COOH
Arginine | H2NC (NH) NH (CH2)3 CH (NH2) COOH
Glycine | H2NCH2COOH
Proline | [(CH2)3 NH CH] COOH
Serine | HOCH2CH (NH2) COOH
Tyrosine | [C6H4 (OH)] CH2CH (NH2) COOH

The injection port chamber contains dextrose with calcium. The formula for Calcium Chloride is: CaCl2•2H2O. Dextrose, USP, is chemically designated D-glucose, monohydrate (C6H12O6 • H2O) and has the following structure:

Dextrose is derived from corn.

See Table 7 for composition, pH, osmolarity, ionic concentration and caloric content of the admixed product [see Dosage Forms and Strengths (3)].

The dual chamber container is a lipid-compatible plastic container (PL 2401 Plastic).

CLINIMIX E contains no more than 25 mcg/L of aluminum.

12 CLINICAL PHARMACOLOGY

12.1 Mechanism of Action

CLINIMIX E is used as a supplement of nutrition in patients, providing macronutrients (amino acids and dextrose) and micronutrients (electrolytes) parenterally.

The amino acids provide the structural units that make up proteins and are used to synthesize proteins and other biomolecules or are oxidized to urea and carbon dioxide as a source of energy.

The administered dextrose is oxidized to carbon dioxide and water, yielding energy.

12.3 Pharmacokinetics

The disposition of infused amino acids, dextrose, and electrolytes are essentially the same as those absorbed from ordinary food.

16 HOW SUPPLIED/STORAGE AND HANDLING

CLINIMIX E (amino acids with electrolytes in dextrose with calcium) injection (sulfite-free) is available in 1000 mL and 2000 mL volumes (See Table 9).

Table 9: CLINIMIX E Formulations (per 07-19-00-4607 and BE-30-03-649)
After mixing, the product represents | 1000 mL Code and NDC Number | 2000 mL Code and NDC Number
CLINIMIX E 2.75/5 sulfite-free (2.75% Amino Acid with Electrolytes in 5% Dextrose with Calcium) Injection | Code 2B7735 NDC 0338-1142-03
CLINIMIX E 4.25/5 sulfite-free (4.25% Amino Acid with Electrolytes in 5% Dextrose with Calcium) Injection | Code 2B7737 NDC 0338-1144-03 | Code 2B7716 NDC 0338-1113-04
CLINIMIX E 4.25/10 sulfite-free (4.25% Amino Acid with Electrolytes in 10% Dextrose with Calcium) Injection | Code 2B7738 NDC 0338-1145-03 | Code 2B7717 NDC 0338-1115-04
CLINIMIX E 5/15 sulfite-free (5% Amino Acid with Electrolytes in 15% Dextrose with Calcium) Injection | Code 2B7740 NDC 0338-1147-03 | Code 2B7721 NDC 0338-1123-04
CLINIMIX E 5/20 sulfite-free (5% Amino Acid with Electrolytes in 20% Dextrose with Calcium) Injection | Code 2B7741 NDC 0338-1148-03 | Code 2B7722 NDC 0338-1125-04
CLINIMIX E 8/10 sulfite-free (8% Amino Acid with Electrolytes in 10% Dextrose with Calcium) Injection | Code EADB9943 NDC 0338-210-06 | Code EADB9945 NDC 0338-0214-04
CLINIMIX E 8/14 sulfite-free (8% Amino Acid with Electrolytes in 14% Dextrose with Calcium) Injection | Code EADB9963 NDC 0338-0202-06 | Code EADB9965 NDC 0338-0206-04

Table 9: CLINIMIX E Formulations (per BE-30-04-048)
After mixing, the product represents | 1000 mL Code and NDC Number | 2000 mL Code and NDC Number
CLINIMIX E 2.75/5 sulfite-free (2.75% Amino Acid with Electrolytes in 5% Dextrose with Calcium) Injection | Code 2B7735L NDC 0338-7020-01 | /
CLINIMIX E 4.25/5 sulfite-free (4.25% Amino Acid with Electrolytes in 5% Dextrose with Calcium) Injection | Code 2B7737L NDC 0338-7022-01 | Code 2B7716L NDC 0338-7024-01
CLINIMIX E 4.25/10 sulfite-free (4.25% Amino Acid with Electrolytes in 10% Dextrose with Calcium) Injection | Code 2B7738L NDC 0338-7026-01 | Code 2B7717L NDC 0338-7028-01
CLINIMIX E 5/15 sulfite-free (5% Amino Acid with Electrolytes in 15% Dextrose with Calcium) Injection | Code 2B7740L NDC 0338-7030-01 | Code 2B7721L NDC 0338-7032-01
CLINIMIX E 5/20 sulfite-free (5% Amino Acid with Electrolytes in 20% Dextrose with Calcium) Injection | Code 2B7741L NDC 0338-7034-01 | Code 2B7722L NDC 0338-7036-01
CLINIMIX E 8/10 sulfite-free (8% Amino Acid with Electrolytes in 10% Dextrose with Calcium) Injection | Code EADB9943 NDC 0338-0210-06 | Code EADB9945 NDC 0338-0214-04
CLINIMIX E 8/14 sulfite-free (8% Amino Acid with Electrolytes in 14% Dextrose with Calcium) Injection | Code EADB9963 NDC 0338-0202-06 | Code EADB9965 NDC 0338-0206-04

Minimize exposure of CLINIMIX E to heat and avoid excessive heat.

Protect from freezing.

Store CLINIMIX E at room temperature (25°C/77°F) (may briefly store at up to 40°C/104°F).

Refrigerated storage is limited to 9 days once the protective overwrap has been opened.

Do not use if the protective overwrap has been previously opened or damaged.

For storage of admixed solutions see Dosage and Administration (2.3, 2.4).

17 PATIENT COUNSELING INFORMATION

Inform patients, caregivers, or home healthcare providers of the following risks of CLINIMIX E:

- Pulmonary embolism due to pulmonary vascular precipitates [see Warnings and Precautions (5.1)]
- Death in neonates due to calcium-ceftriaxone precipitates [see Warnings and Precautions (5.2)]
- Hypersensitivity reactions [see Warnings and Precautions (5.3)]
- Risk of Infections [see Warnings and Precautions (5.4)]
- Refeeding syndrome [see Warnings and Precautions (5.5)]
- Hyperglycemia or hyperosmolar hyperglycemic state [see Warnings and Precautions (5.6)]
- Vein damage and thrombosis [see Warnings and Precautions (5.7)]
- Hepatobiliary disorders [see Warnings and Precautions (5.8)]
- Aluminum toxicity [see Warnings and Precautions (5.9)]
- Parenteral Nutrition Associated Liver Disease (PNALD) [see Warnings and Precautions (5.10)]
- Electrolyte imbalance and fluid overload [see Warnings and Precautions (5.11)]

Baxter Healthcare Corporation
  Deerfield, IL 60015 USA
  Baxter and Clinimix E are registered trademarks of Baxter International Inc.
07-19-00-4607 [Applies to Baxter Healthcare Corporation, Jayuya – Puerto Rico manufacturing plant]
  BE-30-03-649 [Applies to Baxter SA, Lessines – Belgium manufacturing plant for Clinimix E 8/20 and Clinimix E 8/14]
  BE-30-04-048 [Applies to Baxter SA, Lessines – Belgium manufacturing plant for the other Clinimix E formulations]

PACKAGE LABEL - PRINCIPAL DISPLAY PANEL

Container Label

LOT EXP

2B7735 NDC 0338-1142-03

CLINIMIX E
WITH ELECTROLYTES 2.75/5

SULFITE-FREE
(2.75% Amino Acids
with Electrolytes in
5% Dextrose with
Calcium) Injection

500 mL INJECTION PORT CHAMBER
10% Dextrose Injection with Calcium

500 mL OUTLET PORT CHAMBER
5.5% Amino Acid Injection

Rx Only

ACTIVATE SEAL AND
MIX THOROUGHLY BEFORE USE

SEE PRESRCIBING INFORMATION FOR INSTRUCTIONS
ON ACTIVATION

AFTER MIXING THE PRODUCT REPRESENTS 1000 mL

REFRIGERATED STORAGE IS LIMITED TO 9 DAYS

A SLIGHT YELLOW COLOR DOES NOT ALTER THE QUALITY
AND EFFICACY OF THIS PRODUCT

ASK PHARMACIST ABOUT ADDITIVE COMPATIBILITY

CONTENTS OF EACH 100 mL OF THE ADMIXED
INJECTION

DEXTROSE HYDROUS USP 5 g
ESSENTIAL AMINO ACIDS
LEUCINE 201 mg
ISOLEUCINE 165 mg
VALINE 160 mg
LYSINE (ADDED AS THE HYDROCHLORIDE SALT) 159 mg
PHENYLALANINE 154 mg
HISTIDINE 132 mg
THREONINE 116 mg
METHIONINE 110 mg
TRYPTOPHAN 50 mg
NONESSENTIAL AMINO ACIDS
ALANINE 570 mg
ARGININE 316 mg
GLYCINE 283 mg
PROLINE 187 mg
SERINE 138 mg
TYROSINE 11 mg
ELECTROLYTES
SODIUM ACETATE TRIHYDRATE USP 217 mg
DIBASIC POTASSIUM PHOSPHATE USP 261 mg
SODIUM CHLORIDE USP 112 mg
MAGNESIUM CHLORIDE USP 51 mg
CALCIUM CHLORIDE DIHYDRATE USP 33 mg
mEq/L
SODIUM 35
POTASSIUM 30
MAGNESIUM 5
CALCIUM 4.5 (2.2 mmol/L)
ACETATE 51
CHLORIDE 39
PHOSPHATE 30 (15 mmol/L)
BALANCED BY IONS FROM AMINO ACIDS
pH ADJUSTED WITH GLACIAL ACETIC ACID
STERILE
SINGLE DOSE CONTAINER

ROOM TEMPERATURE (25°C/77°F)
AVOID EXCESSIVE HEAT
PROTECT FROM FREEZING
SEE PRESCRIBING INFORMATION

BAXTER LOGO
BAXTER HEALTHCARE CORPORATION
DEERFIELD IL 60015 US
MADE IN USA

Container Label

LOT EXP

2B7737 NDC 0338-1144-03

CLINIMIX E
WITH ELECTROLYTES 4.25/5

SULFITE-FREE
(4.25% Amino Acid
with Electrolytes in
5% Dextrose with
Calcium) Injection

500 mL INJECTION PORT CHAMBER
10% Dextrose Injection with Calcium

500 mL OUTLET PORT CHAMBER
8.5% Amino Acid Injection

Rx Only

ACTIVATE SEAL AND
MIX THOROUGHLY BEFORE USE

SEE PRESRCIBING INFORMATION FOR INSTRUCTIONS
ON ACTIVATION

AFTER MIXING THE PRODUCT REPRESENTS 1000 mL

REFRIGERATED STORAGE IS LIMITED TO 9 DAYS

A SLIGHT YELLOW COLOR DOES NOT ALTER THE
QUALITY AND EFFICACY OF THIS PRODUCT

ASK PHARMACIST ABOUT ADDITIVE COMPATIBILITY

CONTENTS OF EACH 100 mL OF THE ADMIXED
INJECTION

DEXTROSE HYDROUS USP 5 g
ESSENTIAL AMINO ACIDS
LEUCINE 311 mg
ISOLEUCINE 255 mg
VALINE 247 mg
LYSINE (ADDED AS THE HYDROCHLORIDE SALT) 247 mg
PHENYLALANINE 238 mg
HISTIDINE 204 mg
THREONINE 179 mg
METHIONINE 170 mg
TRYPTOPHAN 77 mg
NONESSENTIAL AMINO ACIDS
ALANINE 880 mg
ARGININE 489 mg
GLYCINE 438 mg
PROLINE 289 mg
SERINE 213 mg
TYROSINE 17 mg
ELECTROLYTES
SODIUM ACETATE TRIHYDRATE USP 297 mg
DIBASIC POTASSIUM PHOSPHATE USP 261 mg
SODIUM CHLORIDE USP 77 mg
MAGNESIUM CHLORIDE USP 51 mg
CALCIUM CHLORIDE DIHYDRATE USP 33 mg
mEq/L
SODIUM 35
POTASSIUM 30
MAGNESIUM 5
CALCIUM 4.5 (2.2 mmol/L)
ACETATE 70
CHLORIDE 39
PHOSPHATE 30 (15 mmol/L)
BALANCED BY IONS FROM AMINO ACIDS
pH ADJUSTED WITH GLACIAL ACETIC ACID
STERILE
SINGLE DOSE CONTAINER
ROOM TEMPERATURE (25°C/77°F)
AVOID EXCESSIVE HEAT
PROTECT FROM FREEZING
SEE PRESCRIBING INFORMATION

BAXTER LOGO
BAXTER HEALTHCARE CORPORATION
DEERFIELD IL 60015 US
MADE IN USA

Container Label

LOT EXP

2B7716 NDC 0338-1113-04

CLINIMIX E
WITH ELECTROLYTES 4.25/5

SULFITE-FREE
(4.25% Amino Acid
with Electrolytes in
5% Dextrose with
Calcium) Injection

1000 mL INJECTION PORT CHAMBER
10% Dextrose Injection with Calcium

1000 mL OUTLET PORT CHAMBER
8.5% Amino Acid Injection

Rx Only

ACTIVATE SEAL AND
MIX THOROUGHLY BEFORE USE

SEE PRESRCIBING INFORMATION FOR INSTRUCTIONS
ON ACTIVATION

AFTER MIXING THE PRODUCT REPRESENTS 2000 mL

REFRIGERATED STORAGE IS LIMITED TO 9 DAYS

A SLIGHT YELLOW COLOR DOES NOT ALTER THE
QUALITY AND EFFICACY OF THIS PRODUCT

ASK PHARMACIST ABOUT ADDITIVE COMPATIBILITY

CONTENTS OF EACH 100 mL OF THE ADMIXED
INJECTION

DEXTROSE HYDROUS USP 5 g
ESSENTIAL AMINO ACIDS
LEUCINE 311 mg
ISOLEUCINE 255 mg
VALINE 247 mg
LYSINE (ADDED AS THE HYDROCHLORIDE SALT) 247 mg
PHENYLALANINE 238 mg
HISTIDINE 204 mg
THREONINE 179 mg
METHIONINE 170 mg
TRYPTOPHAN 77 mg
NONESSENTIAL AMINO ACIDS
ALANINE 880 mg
ARGININE 489 mg
GLYCINE 438 mg
PROLINE 289 mg
SERINE 213 mg
TYROSINE 17 mg
ELECTROLYTES
SODIUM ACETATE TRIHYDRATE USP 297 mg
DIBASIC POTASSIUM PHOSPHATE USP 261 mg
SODIUM CHLORIDE USP 77 mg
MAGNESIUM CHLORIDE USP 51 mg
CALCIUM CHLORIDE DIHYDRATE USP 33 mg
mEq/L
SODIUM 35
POTASSIUM 30
MAGNESIUM 5
CALCIUM 4.5 (2.2 mmol/L)
ACETATE 70
CHLORIDE 39
PHOSPHATE 30 (15 mmol/L)
BALANCED BY IONS FROM AMINO ACIDS
pH ADJUSTED WITH GLACIAL ACETIC ACID
STERILE
SINGLE DOSE CONTAINER

ROOM TEMPERATURE (25°C/77°F)

AVOID EXCESSIVE HEAT

PROTECT FROM FREEZING

SEE PRESCRIBING INFORMATION

BAXTER LOGO
BAXTER HEALTHCARE CORPORATION
DEERFIELD IL 60015 US

Container Label

LOT EXP

2B7738 NDC 0338-1145-03

CLINIMIX E
WITH ELECTROLYTES 4.25/10

SULFITE-FREE
(4.25% Amino Acid
with Electrolytes in
10% Dextrose with
Calcium) Injection

500 mL INJECTION PORT CHAMBER
20% Dextrose Injection with Calcium

500 mL OUTLET PORT CHAMBER
8.5% Amino Acid Injection

Rx Only

ACTIVATE SEAL AND
MIX THOROUGHLY BEFORE USE

SEE PRESRCIBING INFORMATION FOR INSTRUCTIONS
ON ACTIVATION

AFTER MIXING THE PRODUCT REPRESENTS 1000 mL

REFRIGERATED STORAGE IS LIMITED TO 9 DAYS

A SLIGHT YELLOW COLOR DOES NOT ALTER THE
QUALITY AND EFFICACY OF THIS PRODUCT

ASK PHARMACIST ABOUT ADDITIVE COMPATIBILITY

CONTENTS OF EACH 100 mL OF THE ADMIXED
INJECTION

DEXTROSE HYDROUS USP 10 g
ESSENTIAL AMINO ACIDS
LEUCINE 311 mg
ISOLEUCINE 255 mg
VALINE 247 mg
LYSINE (ADDED AS THE HYDROCHLORIDE SALT) 247 mg
PHENYLALANINE 238 mg
HISTIDINE 204 mg
THREONINE 179 mg
METHIONINE 170 mg
TRYPTOPHAN 77 mg
NONESSENTIAL AMINO ACIDS
ALANINE 880 mg
ARGININE 489 mg
GLYCINE 438 mg
PROLINE 289 mg
SERINE 213 mg
TYROSINE 17 mg
ELECTROLYTES
SODIUM ACETATE TRIHYDRATE USP 297 mg
DIBASIC POTASSIUM PHOSPHATE USP 261 mg
SODIUM CHLORIDE USP 77 mg
MAGNESIUM CHLORIDE USP 51 mg
CALCIUM CHLORIDE DIHYDRATE USP 33 mg
mEq/L
SODIUM 35
POTASSIUM 30
MAGNESIUM 5
CALCIUM 4.5 (2.2 mmol/L)
ACETATE 70
CHLORIDE 39
PHOSPHATE 30 (15 mmol/L)
BALANCED BY IONS FROM AMINO ACIDS
pH ADJUSTED WITH GLACIAL ACETIC ACID
STERILE
SINGLE DOSE CONTAINER
ROOM TEMPERATURE (25°C/77°F)
AVOID EXCESSIVE HEAT
PROTECT FROM FREEZING
SEE PRESCRIBING INFORMATION

BAXTER LOGO
BAXTER HEALTHCARE CORPORATION
DEERFIELD IL 60015 US

Container Label

LOT EXP

2B7717 NDC 0338-1115-04

CLINIMIX E
WITH ELECTROLYTES 4.25/10

SULFITE-FREE
(4.25% Amino Acid
with Electrolytes in
10% Dextrose with
Calcium) Injection

CENTRAL LINE INFUSION ONLY

1000 mL INJECTION PORT CHAMBER
20% Dextrose Injection with Calcium

1000 mL OUTLET PORT CHAMBER
8.5% Amino Acid Injection

Rx Only

ACTIVATE SEAL AND
MIX THOROUGHLY BEFORE USE

SEE PRESRCIBING INFORMATION FOR INSTRUCTIONS
ON ACTIVATION

AFTER MIXING THE PRODUCT REPRESENTS 2000 mL

REFRIGERATED STORAGE IS LIMITED TO 9 DAYS

A SLIGHT YELLOW COLOR DOES NOT ALTER THE
QUALITY AND EFFICACY OF THIS PRODUCT

ASK PHARMACIST ABOUT ADDITIVE COMPATIBILITY

CONTENTS OF EACH 100 mL OF THE ADMIXED
INJECTION

DEXTROSE HYDROUS USP 10 g
ESSENTIAL AMINO ACIDS
LEUCINE 311 mg
ISOLEUCINE 255 mg
VALINE 247 mg
LYSINE (ADDED AS THE HYDROCHLORIDE SALT) 247 mg
PHENYLALANINE 238 mg
HISTIDINE 204 mg
THREONINE 179 mg
METHIONINE 170 mg
TRYPTOPHAN 77 mg
NONESSENTIAL AMINO ACIDS
ALANINE 880 mg
ARGININE 489 mg
GLYCINE 438 mg
PROLINE 289 mg
SERINE 213 mg
TYROSINE 17 mg
ELECTROLYTES
SODIUM ACETATE TRIHYDRATE USP 297 mg
DIBASIC POTASSIUM PHOSPHATE USP 261 mg
SODIUM CHLORIDE USP 77 mg
MAGNESIUM CHLORIDE USP 51 mg
CALCIUM CHLORIDE DIHYDRATE USP 33 mg
mEq/L
SODIUM 35
POTASSIUM 30
MAGNESIUM 5
CALCIUM 4.5 (2.2 mmol/L)
ACETATE 70
CHLORIDE 39
PHOSPHATE 30 (15 mmol/L)
BALANCED BY IONS FROM AMINO ACIDS
pH ADJUSTED WITH GLACIAL ACETIC ACID
STERILE
SINGLE DOSE CONTAINER

ROOM TEMPERATURE (25°C/77°F)

AVOID EXCESSIVE HEAT

PROTECT FROM FREEZING

SEE PRESCRIBING INFORMATION

BAXTER LOGO
BAXTER HEALTHCARE CORPORATION
DEERFIELD IL 60015 US

Container Label

LOT EXP

2B7740 NDC 0338-1147-03

CLINIMIX E
WITH ELECTROLYTES 5/15

SULFITE-FREE
(5% Amino Acid
with Electrolytes in
15% Dextrose with
Calcium) Injection

CENTRAL LINE INFUSION ONLY

500 mL INJECTION PORT CHAMBER
30% Dextrose Injection with Calcium

500 mL OUTLET PORT CHAMBER
10% Amino Acid Injection

Rx Only

ACTIVATE SEAL AND
MIX THOROUGHLY BEFORE USE

SEE PRESRCIBING INFORMATION FOR INSTRUCTIONS
ON ACTIVATION

AFTER MIXING THE PRODUCT REPRESENTS 1000 mL

REFRIGERATED STORAGE IS LIMITED TO 9 DAYS

A SLIGHT YELLOW COLOR DOES NOT ALTER THE
QUALITY AND EFFICACY OF THIS PRODUCT

ASK PHARMACIST ABOUT ADDITIVE COMPATIBILITY

CONTENTS OF EACH 100 mL OF THE ADMIXED
INJECTION

DEXTROSE HYDROUS USP 15 g
ESSENTIAL AMINO ACIDS
LEUCINE 365 mg
ISOLEUCINE 300 mg
VALINE 290 mg
LYSINE (ADDED AS THE HYDROCHLORIDE SALT) 290 mg
PHENYLALANINE 280 mg
HISTIDINE 240 mg
THREONINE 210 mg
METHIONINE 200 mg
TRYPTOPHAN 90 mg
NONESSENTIAL AMINO ACIDS
ALANINE 1035 mg
ARGININE 575 mg
GLYCINE 515 mg
PROLINE 340 mg
SERINE 250 mg
TYROSINE 20 mg
ELECTROLYTES
SODIUM ACETATE TRIHYDRATE USP 340 mg
DIBASIC POTASSIUM PHOSPHATE USP 261 mg
SODIUM CHLORIDE USP 59 mg
MAGNESIUM CHLORIDE USP 51 mg
CALCIUM CHLORIDE DIHYDRATE USP 33 mg
mEq/L
SODIUM 35
POTASSIUM 30
MAGNESIUM 5
CALCIUM 4.5 (2.2 mmol/L)
ACETATE 80
CHLORIDE 39
PHOSPHATE 30 (15 mmol/L)
BALANCED BY IONS FROM AMINO ACIDS
pH ADJUSTED WITH GLACIAL ACETIC ACID
STERILE
SINGLE DOSE CONTAINER

ROOM TEMPERATURE (25°C/77°F)
AVOID EXCESSIVE HEAT
PROTECT FROM FREEZING
SEE PRESCRIBING INFORMATION

BAXTER LOGO
BAXTER HEALTHCARE CORPORATION
DEERFIELD IL 60015 US

Container Label

Container Label

LOT EXP

2B7721 NDC 0338-1123-04

CLINIMIX E
WITH ELECTROLYTES 5/15

SULFITE-FREE
(5% Amino Acid
with Electrolytes in
15% Dextrose with
Calcium) Injection

1000 mL INJECTION PORT CHAMBER
30% Dextrose Injection with Calcium

1000 mL OUTLET PORT CHAMBER
10% Amino Acid Injection

Rx Only

ACTIVATE SEAL AND
MIX THOROUGHLY BEFORE USE

SEE PRESRCIBING INFORMATION FOR INSTRUCTIONS
ON ACTIVATION

AFTER MIXING THE PRODUCT REPRESENTS 2000 mL

REFRIGERATED STORAGE IS LIMITED TO 9 DAYS

A SLIGHT YELLOW COLOR DOES NOT ALTER THE
QUALITY AND EFFICACY OF THIS PRODUCT

ASK PHARMACIST ABOUT ADDITIVE COMPATIBILITY

CONTENTS OF EACH 100 mL OF THE ADMIXED
INJECTION

DEXTROSE HYDROUS USP 15 g
ESSENTIAL AMINO ACIDS
LEUCINE 365 mg
ISOLEUCINE 300 mg
VALINE 290 mg
LYSINE (ADDED AS THE HYDROCHLORIDE SALT) 290 mg
PHENYLALANINE 280 mg
HISTIDINE 240 mg
THREONINE 210 mg
METHIONINE 200 mg
TRYPTOPHAN 90 mg
NONESSENTIAL AMINO ACIDS
ALANINE 1035 mg
ARGININE 575 mg
GLYCINE 515 mg
PROLINE 340 mg
SERINE 250 mg
TYROSINE 20 mg
ELECTROLYTES
SODIUM ACETATE TRIHYDRATE USP 340 mg
DIBASIC POTASSIUM PHOSPHATE USP 261 mg
SODIUM CHLORIDE USP 59 mg
MAGNESIUM CHLORIDE USP 51 mg
CALCIUM CHLORIDE DIHYDRATE USP 33 mg
mEq/L
SODIUM 35
POTASSIUM 30
MAGNESIUM 5
CALCIUM 4.5 (2.2 mmol/L)
ACETATE 80
CHLORIDE 39
PHOSPHATE 30 (15 mmol/L)
BALANCED BY IONS FROM AMINO ACIDS
pH ADJUSTED WITH GLACIAL ACETIC ACID
STERILE
SINGLE DOSE CONTAINER

ROOM TEMPERATURE (25°C/77°F)

AVOID EXCESSIVE HEAT

PROTECT FROM FREEZING

SEE PRESCRIBING INFORMATION

BAXTER LOGO
BAXTER HEALTHCARE CORPORATION
DEERFIELD IL 60015 US

Container Label

LOT EXP

2B7741 NDC 0338-1148-03

CLINIMIX E
WITH ELECTROLYTES 5/20

SULFITE-FREE
(5% Amino Acid
with Electrolytes in
20% Dextrose with
Calcium) Injection

500 mL INJECTION PORT CHAMBER
40% Dextrose Injection with Calcium

500 mL OUTLET PORT CHAMBER
10% Amino Acid Injection

Rx Only

ACTIVATE SEAL AND
MIX THOROUGHLY BEFORE USE

SEE PRESRCIBING INFORMATION FOR INSTRUCTIONS
ON ACTIVATION

AFTER MIXING THE PRODUCT REPRESENTS 1000 mL

REFRIGERATED STORAGE IS LIMITED TO 9 DAYS

A SLIGHT YELLOW COLOR DOES NOT ALTER THE
QUALITY AND EFFICACY OF THIS PRODUCT

ASK PHARMACIST ABOUT ADDITIVE COMPATIBILITY

CONTENTS OF EACH 100 mL OF THE ADMIXED
INJECTION

DEXTROSE HYDROUS USP 20 g
ESSENTIAL AMINO ACIDS
LEUCINE 365 mg
ISOLEUCINE 300 mg
VALINE 290 mg
LYSINE (ADDED AS THE HYDROCHLORIDE SALT) 290 mg
PHENYLALANINE 280 mg
HISTIDINE 240 mg
THREONINE 210 mg
METHIONINE 200 mg
TRYPTOPHAN 90 mg
NONESSENTIAL AMINO ACIDS
ALANINE 1035 mg
ARGININE 575 mg
GLYCINE 515 mg
PROLINE 340 mg
SERINE 250 mg
TYROSINE 20 mg
ELECTROLYTES
SODIUM ACETATE TRIHYDRATE USP 340 mg
DIBASIC POTASSIUM PHOSPHATE USP 261 mg
SODIUM CHLORIDE USP 59 mg
MAGNESIUM CHLORIDE USP 51 mg
CALCIUM CHLORIDE DIHYDRATE USP 33 mg
mEq/L
SODIUM 35
POTASSIUM 30
MAGNESIUM 5
CALCIUM 4.5 (2.2 mmol/L)
ACETATE 80
CHLORIDE 39
PHOSPHATE 30 (15 mmol/L)
BALANCED BY IONS FROM AMINO ACIDS
pH ADJUSTED WITH GLACIAL ACETIC ACID
STERILE
SINGLE DOSE CONTAINER
ROOM TEMPERATURE (25°C/77°F)
AVOID EXCESSIVE HEAT
PROTECT FROM FREEZING
SEE PRESCRIBING INFORMATION

BAXTER LOGO
BAXTER HEALTHCARE CORPORATION
DEERFIELD IL 60015 US

Container Label

LOT EXP

2B7722 NDC 0338-1125-04

CLINIMIX E
WITH ELECTROLYTES 5/20

SULFITE-FREE
(5% Amino Acid
with Electrolytes in
20% Dextrose with
Calcium) Injection

1000 mL INJECTION PORT CHAMBER
40% Dextrose Injection with Calcium

1000 mL OUTLET PORT CHAMBER
10% Amino Acid Injection

Rx Only

ACTIVATE SEAL AND
MIX THOROUGHLY BEFORE USE

SEE PRESRCIBING INFORMATION FOR INSTRUCTIONS
ON ACTIVATION

AFTER MIXING THE PRODUCT REPRESENTS 2000 mL

REFRIGERATED STORAGE IS LIMITED TO 9 DAYS

A SLIGHT YELLOW COLOR DOES NOT ALTER THE
QUALITY AND EFFICACY OF THIS PRODUCT

ASK PHARMACIST ABOUT ADDITIVE COMPATIBILITY

CONTENTS OF EACH 100 mL OF THE ADMIXED
INJECTION

DEXTROSE HYDROUS USP 20 g
ESSENTIAL AMINO ACIDS
LEUCINE 365 mg
ISOLEUCINE 300 mg
VALINE 290 mg
LYSINE (ADDED AS THE HYDROCHLORIDE SALT) 290 mg
PHENYLALANINE 280 mg
HISTIDINE 240 mg
THREONINE 210 mg
METHIONINE 200 mg
TRYPTOPHAN 90 mg
NONESSENTIAL AMINO ACIDS
ALANINE 1035 mg
ARGININE 575 mg
GLYCINE 515 mg
PROLINE 340 mg
SERINE 250 mg
TYROSINE 20 mg
ELECTROLYTES
SODIUM ACETATE TRIHYDRATE USP 340 mg
DIBASIC POTASSIUM PHOSPHATE USP 261 mg
SODIUM CHLORIDE USP 59 mg
MAGNESIUM CHLORIDE USP 51 mg
CALCIUM CHLORIDE DIHYDRATE USP 33 mg
mEq/L
SODIUM 35
POTASSIUM 30
MAGNESIUM 5
CALCIUM 4.5 (2.2 mmol/L)
ACETATE 80
CHLORIDE 39
PHOSPHATE 30 (15 mmol/L)
BALANCED BY IONS FROM AMINO ACIDS
pH ADJUSTED WITH GLACIAL ACETIC ACID
STERILE
SINGLE DOSE CONTAINER

ROOM TEMPERATURE (25°C/77°F)

AVOID EXCESSIVE HEAT

PROTECT FROM FREEZING

SEE PRESCRIBING INFORMATION

BAXTER LOGO
BAXTER HEALTHCARE CORPORATION
DEERFIELD IL 60015 US

Container Label

EADB9963

1000 mL

NDC 0338-0202-01

CLINIMIX E
WITH ELECTROLYTES 8/14

SULFITE-FREE
(8% Amino Acids
with Electrolytes in
14% Dextrose with
Calcium) Injection

CENTRAL LINE INFUSION ONLY

360 mL INJECTION PORT CHAMBER
39% Dextrose Injection with Calcium

640 mL OUTLET PORT CHAMBER

12.5% Amino Acid Injection

with Electrolytes

Rx Only

ACTIVATE SEAL AND
MIX THOROUGHLY BEFORE USE

2000 mL

SEE PRESCRIBING INFORMATION FOR INSTRUCTIONS
ON ACTIVATION

AFTER MIXING THE PRODUCT REPRESENTS 1000 mL

REFRIGERATED STORAGE IS LIMITED TO 9 DAYS
ONCE OVERWRAP IS OPENED

A SLIGHT YELLOW COLOR DOES NOT ALTER THE
QUALITY AND EFFICACY OF THIS PRODUCT

ASK PHARMACIST ABOUT ADDITIVE COMPATIBILITY

EXP

CONTENTS OF EACH 100 mL
OF THE ADMIXED INJECTION
DEXTROSE HYDROUS USP 14 g
ESSENTIAL AMINO ACIDS
LEUCINE 584 mg
ISOLEUCINE 480 mg
VALINE 464 mg
LYSINE (ADDED AS THE
HYDROCHLORIDE SALT) 464 mg
PHENYLALANINE 448 mg
HISTIDINE 384 mg
THREONINE 336 mg
METHIONINE 320 mg
TRYPTOPHAN 144 mg
NONESSENTIAL AMINO ACIDS
ALANINE 1656 mg
ARGININE 920 mg
GLYCINE 824 mg
PROLINE 544 mg
SERINE 400 mg
TYROSINE 32 mg
ELECTROLYTES
DIBASIC POTASSIUM
PHOSPHATE USP 261 mg
SODIUM CHLORIDE USP 205 mg
MAGNESIUM CHLORIDE USP 51 mg
CALCIUM CHLORIDE
DIHYDRATE USP 33 mg
mEq/L
SODIUM 35
POTASSIUM 30
MAGNESIUM 5
CALCIUM 4.5 (2.2 mmol/L)
ACETATE 83
CHLORIDE 76
PHOSPHATE 30 (15 mmol/L)

BALANCED BY IONS FROM AMINO ACIDS

pH ADJUSTED WITH GLACIAL ACETIC ACID AND HYDROCHLORIC ACID

STERILE

SINGLE DOSE CONTAINER

STORE AT ROOM TEMPERATURE (25ºC/77ºF)
IN UNOPENED OVERWRAP

AVOID EXCESSIVE HEAT

PROTECT FROM FREEZING

SEE PRESCRIBING INFORMATION

BAXTER LOGo
BAXTER HEALTHCARE CORPORATION
DEERFIELD IL 60015 USA
MADE IN BELGIUM

LOT

BE-35-04-044

Container Label

EADB9965

2000 mL

NDC 0338-0206-01

CLINIMIX E
WITH ELECTROLYTES 8/14

SULFITE-FREE
(8% Amino Acids
with Electrolytes in
14% Dextrose with
Calcium) Injection

CENTRAL LINE INFUSION ONLY

720 mL INJECTION PORT CHAMBER

39% Dextrose Injection with Calcium

1280 mL OUTLET PORT CHAMBER

12.5% Amino Acid Injection
with Electrolytes

Rx Only

ACTIVATE SEAL AND
MIX THOROUGHLY BEFORE USE

SEE PRESCRIBING INFORMATION FOR INSTRUCTIONS ON ACTIVATION

AFTER MIXING THE PRODUCT REPRESENTS 2000 mL

REFRIGERATED STORAGE IS LIMITED TO 9 DAYS
ONCE OVERWRAP IS OPENED

A SLIGHT YELLOW COLOR DOES NOT ALTER THE QUALITY AND
EFFICACY OF THIS PRODUCT

ASK PHARMACIST ABOUT ADDITIVE COMPATIBILITY

EADB9965

Exp

CONTENTS OF EACH 100 mL OF THE
ADMIXED INJECTION
DEXTROSE HYDROUS USP 14 g

ESSENTIAL AMINO ACIDS
LEUCINE 584 mg
ISOLEUCINE 480 mg
VALINE 464 mg
LYSINE (ADDED AS THE
HYDROCHLORIDE SALT) 464 mg
PHENYLALANINE 448 mg
HISTIDINE 384 mg
THREONINE 336 mg
METHIONINE 320 mg
TRYPTOPHAN 144 mg

NONESSENTIAL AMINO ACIDS
ALANINE 1656 mg
ARGININE 920 mg
GLYCINE 824 mg
PROLINE 544 mg
SERINE 400 mg
TYROSINE 32 mg

ELECTROLYTES
DIBASIC POTASSIUM
PHOSPHATE USP 261 mg
SODIUM CHLORIDE USP 205 mg
MAGNESIUM CHLORIDE USP 51 mg
CALCIUM CHLORIDE
DIHYDRATE USP 33 mg

mEq/L
SODIUM 35
POTASSIUM 30
MAGNESIUM 5
CALCIUM 4.5 (2.2 mmol/L)
ACETATE 83
CHLORIDE 76
PHOSPHATE 30 (15 mmol/L)

BALANCED BY IONS FROM AMINO ACIDS

pH ADJUSTED WITH GLACIAL ACETIC ACID
AND HYDROCHLORIC ACID

STERILE

SINGLE DOSE CONTAINER

STORE AT ROOM TEMPERATURE (25ºC/77ºF)
IN UNOPENED OVERWRAP

AVOID EXCESSIVE HEAT

PROTECT FROM FREEZING

SEE PRESCRIBING INFORMATION

BAXTER LOGO
BAXTER HEALTHCARE CORPORATION
DEERFIELD IL 60015 USA
MADE IN BELGIUM

Lot

BE-35-04-048

Container Label

EADB9943

1000 mL

NDC 0338-0210-01

CLINIMIX E
WITH ELECTROLYTES 8/10

SULFITE-FREE
(8% Amino Acids
with Electrolytes in
10% Dextrose with
Calcium) Injection

CENTRAL LINE INFUSION ONLY

360 mL INJECTION PORT CHAMBER
28% Dextrose Injection with Calcium

640 mL OUTLET PORT CHAMBER
12.5% Amino Acid Injection with Electrolytes

Rx Only

ACTIVATE SEAL AND
MIX THOROUGHLY BEFORE USE

SEE PRESCRIBING INFORMATION FOR INSTRUCTIONS
ON ACTIVATION

AFTER MIXING THE PRODUCT REPRESENTS 1000 mL

REFRIGERATED STORAGE IS LIMITED TO 9 DAYS
ONCE OVERWRAP IS OPENED

A SLIGHT YELLOW COLOR DOES NOT ALTER THE
QUALITY AND EFFICACY OF THIS PRODUCT

ASK PHARMACIST ABOUT ADDITIVE COMPATIBILITY

EXP

CONTENTS OF EACH 100 mL
OF THE ADMIXED INJECTION
DEXTROSE HYDROUS USP 10 g

ESSENTIAL AMINO ACIDS
LEUCINE 584 mg
ISOLEUCINE 480 mg
VALINE 464 mg
LYSINE (ADDED AS THE
HYDROCHLORIDE SALT) 464 mg
PHENYLALANINE 448 mg
HISTIDINE 384 mg
THREONINE 336 mg
METHIONINE 320 mg
TRYPTOPHAN 144 mg

NONESSENTIAL AMINO ACIDS
ALANINE 1656 mg
ARGININE 920 mg
GLYCINE 824 mg
PROLINE 544 mg
SERINE 400 mg
TYROSINE 32 mg

ELECTROLYTES
DIBASIC POTASSIUM
PHOSPHATE USP 261 mg
SODIUM CHLORIDE USP 205 mg
MAGNESIUM CHLORIDE USP 51 mg
CALCIUM CHLORIDE
DIHYDRATE USP 33 mg

mEq/L
SODIUM 35
POTASSIUM 30
MAGNESIUM 5
CALCIUM 4.5 (2.2 mmol/L)
ACETATE 83
CHLORIDE 76
PHOSPHATE 30 (15 mmol/L)

BALANCED BY IONS FROM AMINO ACIDS
pH ADJUSTED WITH GLACIAL ACETIC ACID
AND HYDROCHLORIC ACID
STERILE
SINGLE DOSE CONTAINER
STORE AT ROOM TEMPERATURE (25ºC/77ºF)
IN UNOPENED OVERWRAP
AVOID EXCESSIVE HEAT
PROTECT FROM FREEZING
SEE PRESCRIBING INFORMATION

BAXTER LOGO
BAXTER HEALTHCARE CORPORATION
DEERFIELD IL 60015 USA
MADE IN BELGIUM

LOT

BE-35-04-042

Container Label

EADB9945

2000 mL

NDC 0338-0214-01

CLINIMIX E
WITH ELECTROLYTES 8/10

SULFITE-FREE
(8% Amino Acids
with Electrolytes in
10% Dextrose with
Calcium) Injection

CENTRAL LINE INFUSION ONLY

720 mL INJECTION PORT CHAMBER

28% Dextrose Injection with Calcium

1280 mL OUTLET PORT CHAMBER

12.5% Amino Acid Injection
with Electrolytes

Rx Only

ACTIVATE SEAL AND
MIX THOROUGHLY BEFORE USE

SEE PRESCRIBING INFORMATION FOR INSTRUCTIONS ON ACTIVATION

AFTER MIXING THE PRODUCT REPRESENTS 2000 mL

REFRIGERATED STORAGE IS LIMITED TO 9 DAYS
ONCE OVERWRAP IS OPENED

A SLIGHT YELLOW COLOR DOES NOT ALTER THE QUALITY AND
EFFICACY OF THIS PRODUCT

ASK PHARMACIST ABOUT ADDITIVE COMPATIBILITY

Exp

CONTENTS OF EACH 100 mL OF THE
ADMIXED INJECTION
DEXTROSE HYDROUS USP 10 g

ESSENTIAL AMINO ACIDS
LEUCINE 584 mg
ISOLEUCINE 480 mg
VALINE 464 mg
LYSINE (ADDED AS THE
HYDROCHLORIDE SALT) 464 mg
PHENYLALANINE 448 mg
HISTIDINE 384 mg
THREONINE 336 mg
METHIONINE 320 mg
TRYPTOPHAN 144 mg

NONESSENTIAL AMINO ACIDS
ALANINE 1656 mg
ARGININE 920 mg
GLYCINE 824 mg
PROLINE 544 mg
SERINE 400 mg
TYROSINE 32 mg

ELECTROLYTES
DIBASIC POTASSIUM
PHOSPHATE USP 261 mg
SODIUM CHLORIDE USP 205 mg
MAGNESIUM CHLORIDE USP 51 mg
CALCIUM CHLORIDE
DIHYDRATE USP 33 mg

mEq/L
SODIUM35
POTASSIUM30
MAGNESIUM 5
CALCIUM 4.5 (2.2 mmol/L)
ACETATE 83
CHLORIDE 76
PHOSPHATE 30 (15 mmol/L)

BALANCED BY IONS FROM AMINO ACIDS

pH ADJUSTED WITH GLACIAL ACETIC ACID
AND HYDROCHLORIC ACID

STERILE

SINGLE DOSE CONTAINER

STORE AT ROOM TEMPERATURE (25ºC/77ºF)
IN UNOPENED OVERWRAP

AVOID EXCESSIVE HEAT

PROTECT FROM FREEZING

SEE PRESCRIBING INFORMATION

BAXTER LOGO
BAXTER HEALTHCARE CORPORATION
DEERFIELD IL 60015 USA
MADE IN BELGIUM

Lot

BE35-04-046

Container Label

2B7735L
NDC 0338-7020-01
1000 mL

Barcode
(01) 00303387020013

CLINIMIX E
WITH ELECTROLYTES 2.75/5
SULFITE-FREE

(2.75% Amino Acids with Electrolytes in
5% Dextrose with Calcium) Injection

500 mL INJECTION PORT CHAMBER
10% Dextrose Injection with Calcium

500 mL OUTLET PORT CHAMBER
5.5% Amino Acid Injection

Rx Only

2D Datamatrix (GS1):
NDC, LOT, EXP

2D Datamatrix
Barcode

ACTIVATE SEAL AND
MIX THOROUGHLY BEFORE USE

SEE PRESRCIBING INFORMATION FOR
INSTRUCTIONS ON ACTIVATION

AFTER MIXING THE PRODUCT
REPRESENTS 1000 mL

REFRIGERATED STORAGE IS LIMITED TO
9 DAYS ONCE OVERWRAP IS OPENED

A SLIGHT YELLOW COLOR DOES NOT
ALTER THE QUALITY AND EFFICACY OF
THIS PRODUCT

ASK PHARMACIST ABOUT ADDITIVE
COMPATIBILITY

CONTENTS OF EACH 100 mL OF THE ADMIXED INJECTION
DEXTROSE HYDROUS USP 5 g
ESSENTIAL AMINO ACIDS
LEUCINE 201 mg
ISOLEUCINE 165 mg
VALINE 160 mg
LYSINE (ADDED AS THE
HYDROCHLORIDE SALT) 159 mg
PHENYLALANINE 154 mg
HISTIDINE 132 mg
THREONINE 116 mg
METHIONINE 110 mg
TRYPTOPHAN 50 mg
NONESSENTIAL AMINO ACIDS
ALANINE 570 mg
ARGININE 316 mg
GLYCINE 283 mg
PROLINE 187 mg
SERINE 138 mg
TYROSINE 11 mg
ELECTROLYTES
SODIUM ACETATE TRIHYDRATE USP 216 mg
DIBASIC POTASSIUM PHOSPHATE USP 261 mg
SODIUM CHLORIDE USP 112 mg
MAGNESIUM CHLORIDE USP 51 mg
CALCIUM CHLORIDE DIHYDRATE USP 33 mg
mEq/L
SODIUM 35
POTASSIUM 30
MAGNESIUM 5
CALCIUM 4.5 (2.2 mmol/L)
ACETATE 51
CHLORIDE 39
PHOSPHATE 30 (15 mmol/L)
BALANCED BY IONS FROM AMINO ACIDS
pH ADJUSTED WITH GLACIAL ACETIC ACID
STERILE SINGLE DOSE CONTAINER
STORE AT ROOM TEMPERATURE (25°C/77°F)
AVOID EXCESSIVE HEAT
PROTECT FROM FREEZING
SEE PRESCRIBING INFORMATION

BAXTER LOGO
BAXTER HEALTHCARE CORPORATION
DEERFIELD IL 60015 USA
MADE IN BELGIUM

EXP LOT

1600

1000

800

600

400

BE-35-05-069

200

Container Label

2B7737L
NDC 0338-7022-03
1000 mL

Barcode
(01) 00303387022017

CLINIMIX E
WITH ELECTROLYTES 4.25/5
SULFITE-FREE
(4.25% Amino Acids with Electrolytes in
5% Dextrose with Calcium) Injection

500 mL INJECTION PORT CHAMBER
10% Dextrose Injection with Calcium

500 mL OUTLET PORT CHAMBER
8.5% Amino Acid Injection with Electrolytes

Rx Only

2D Datamatrix (GS1):
NDC, LOT, EXP

2D Datamatrix
Barcode

ACTIVATE SEAL AND
MIX THOROUGHLY BEFORE USE

SEE PRESRCIBING INFORMATION FOR
INSTRUCTIONS ON ACTIVATION

AFTER MIXING THE PRODUCT
REPRESENTS 1000 mL

REFRIGERATED STORAGE IS LIMITED
TO 9 DAYS ONCE OVERWRAP IS OPENED

A SLIGHT YELLOW COLOR DOES NOT
ALTER THE QUALITY AND EFFICACY OF
THIS PRODUCT

ASK PHARMACIST ABOUT ADDITIVE
COMPATIBILITY

CONTENTS OF EACH 100 mL OF THE ADMIXED INJECTION
DEXTROSE HYDROUS USP 5 g
ESSENTIAL AMINO ACIDS
LEUCINE 311 mg
ISOLEUCINE 255 mg
VALINE 247 mg
LYSINE (ADDED AS THE
HYDROCHLORIDE SALT) 247 mg
PHENYLALANINE 238 mg
HISTIDINE 204 mg
THREONINE 179 mg
METHIONINE 170 mg
TRYPTOPHAN 77 mg
NONESSENTIAL AMINO ACIDS
ALANINE 880 mg
ARGININE 489 mg
GLYCINE 438 mg
PROLINE 289 mg
SERINE 213 mg
TYROSINE 17 mg
ELECTROLYTES
SODIUM ACETATE TRIHYDRATE USP 297 mg
DIBASIC POTASSIUM PHOSPHATE USP 261 mg
SODIUM CHLORIDE USP 77 mg
MAGNESIUM CHLORIDE USP 51 mg
CALCIUM CHLORIDE DIHYDRATE USP 33 mg
mEq/L
SODIUM 35
POTASSIUM 30
MAGNESIUM 5
CALCIUM 4.5 (2.2 mmol/L)
ACETATE 70
CHLORIDE 39
PHOSPHATE 30 (15 mmol/L)
BALANCED BY IONS FROM AMINO ACIDS
pH ADJUSTED WITH GLACIAL ACETIC ACID
AND HYDROCHLORIC ACID
STERILE SINGLE DOSE CONTAINER
STORE AT ROOM TEMPERATURE (25°C/77°F)
IN UNOPENED OVERWRAP
AVOID EXCESSIVE HEAT
PROTECT FROM FREEZING
SEE PRESCRIBING INFORMATION

BAXTER LOGO
BAXTER HEALTHCARE CORPORATION
DEERFIELD IL 60015 USA
MADE IN BELGIUM

EXP LOT

1600

1000

800

600

400

BE-35-05-069

200

Container Label

2B7716L
NDC 0338-7024-01
2000 mL

Barcode
(01) 00303387024011

CLINIMIX E
WITH ELECTROLYTES 4.25/5

SULFITE-FREE

(4.25% Amino Acids
with Electrolytes in
5% Dextrose with
Calcium) Injection

1000 mL INJECTION PORT CHAMBER
10% Dextrose Injection with Calcium

1000 mL OUTLET PORT CHAMBER
8.5% Amino Acid Injection with
Electrolytes

Rx Only

ACTIVATE SEAL AND
MIX THOROUGHLY BEFORE USE

SEE PRESRCIBING INFORMATION FOR INSTRUCTIONS
ON ACTIVATION

AFTER MIXING THE PRODUCT REPRESENTS 2000 mL

REFRIGERATED STORAGE IS LIMITED TO
9 DAYS ONCE OVERWRAP IS OPENED

A SLIGHT YELLOW COLOR DOES NOT ALTER THE
QUALITY AND EFFICACY OF THIS PRODUCT

ASK PHARMACIST ABOUT ADDITIVE COMPATIBILITY

2D Datamatrix (GS1):
NDC, LOT, EXP

2D Datamatrix
Barcode

CONTENTS OF EACH 100 mL OF THE ADMIXED
INJECTION
DEXTROSE HYDROUS USP 5 g

ESSENTIAL AMINO ACIDS
LEUCINE 311 mg
ISOLEUCINE 255 mg
VALINE 247 mg
LYSINE (ADDED AS
THE HYDROCHLORIDE SALT) 247 mg
PHENYLALANINE 238 mg
HISTIDINE 204 mg
THREONINE 179 mg
METHIONINE 170 mg
TRYPTOPHAN 77 mg

NONESSENTIAL AMINO ACIDS
ALANINE 880 mg
ARGININE 489 mg
GLYCINE 438 mg
PROLINE 289 mg
SERINE 213 mg
TYROSINE 17 mg

ELECTROLYTES
SODIUM ACETATE
TRIHYDRATE USP 297 mg
DIBASIC POTASSIUM
PHOSPHATE USP 261 mg
SODIUM CHLORIDE USP 77 mg
MAGNESIUM CHLORIDE USP 51 mg
CALCIUM CHLORIDE
DIHYDRATE USP 33 mg

mEq/L
SODIUM 35
POTASSIUM 30
MAGNESIUM 5
CALCIUM 4.5 (2.2 mmol/L)
ACETATE 70
CHLORIDE 39
PHOSPHATE 30 (15 mmol/L)

BALANCED BY IONS FROM AMINO ACIDS
pH ADJUSTED WITH GLACIAL ACETIC ACID
AND HYDROCHLORIC ACID

STERILE
SINGLE DOSE CONTAINER

STORE AT ROOM TEMPERATURE (25°C/77°F)
IN UNOPENED OVERWRAP

AVOID EXCESSIVE HEAT

PROTECT FROM FREEZING

SEE PRESCRIBING INFORMATION

BAXTER LOGO
BAXTER HEALTHCARE CORPORATION
DEERFIELD IL 60015 USA
MADE IN BELGIUM

EXP LOT

2000

1600

1000

800

600

400

BE-35-05-064

200

Container Label

2B7738L
NDC 0338-7026-01
1000 mL

Barcode
(01) 00303387026015

CLINIMIX E
WITH ELECTROLYTES 4.25/10

SULFITE-FREE

(4.25% Amino Acids with Electrolytes in
10% Dextrose with Calcium) Injection

CENTRAL LINE INFUSION ONLY

500 mL INJECTION PORT CHAMBER
20% Dextrose Injection with Calcium

500 mL OUTLET PORT CHAMBER
8.5% Amino Acid Injection with Electrolytes

Rx Only

2D Datamatrix (GS1):
NDC, LOT, EXP

2D Datamatrix
Barcode

ACTIVATE SEAL AND
MIX THOROUGHLY BEFORE USE

SEE PRESRCIBING INFORMATION FOR
INSTRUCTIONS ON ACTIVATION

AFTER MIXING THE PRODUCT
REPRESENTS 1000 mL

REFRIGERATED STORAGE IS LIMITED TO
9 DAYS ONCE OVERWRAP IS OPENED

A SLIGHT YELLOW COLOR DOES NOT
ALTER THE QUALITY AND EFFICACY
OF THIS PRODUCT

ASK PHARMACIST ABOUT ADDITIVE
COMPATIBILITY

CONTENTS OF EACH 100 mL OF THE ADMIXED
INJECTION
DEXTROSE HYDROUS USP 10 g

ESSENTIAL AMINO ACIDS
LEUCINE 311 mg
ISOLEUCINE 255 mg
VALINE 247 mg
LYSINE (ADDED AS THE
HYDROCHLORIDE SALT) 247 mg
PHENYLALANINE 238 mg
HISTIDINE 204 mg
THREONINE 179 mg
METHIONINE 170 mg
TRYPTOPHAN 77 mg

NONESSENTIAL AMINO ACIDS
ALANINE 880 mg
ARGININE 489 mg
GLYCINE 438 mg
PROLINE 289 mg
SERINE 213 mg
TYROSINE 17 mg

ELECTROLYTES
SODIUM ACETATE TRIHYDRATE USP 297 mg
DIBASIC POTASSIUM PHOSPHATE USP 261 mg
SODIUM CHLORIDE USP 77 mg
MAGNESIUM CHLORIDE USP 51 mg
CALCIUM CHLORIDE DIHYDRATE USP 33 mg

mEq/L
SODIUM 35
POTASSIUM 30
MAGNESIUM 5
CALCIUM 4.5 (2.2 mmol/L)
ACETATE 70
CHLORIDE 39
PHOSPHATE 30 (15 mmol/L)
BALANCED BY IONS FROM AMINO ACIDS
pH ADJUSTED WITH GLACIAL ACETIC ACID
AND HYDROCHLORIC ACID

STERILE SINGLE DOSE CONTAINER

STORE AT ROOM TEMPERATURE (25°C/77°F)
IN UNOPENED OVERWRAP
AVOID EXCESSIVE HEAT
PROTECT FROM FREEZING
SEE PRESCRIBING INFORMATION

BAXTER LOGO
BAXTER HEALTHCARE CORPORATION
DEERFIELD IL 60015 USA
MADE IN BELGIUM

EXP LOT

1600

1000

800

600

400

BE-35-05-070

200

Container Label

2B7717L
NDC 0338-7026-01
2000 mL

Barcode
(01) 00303387028019

CLINIMIX E
WITH ELECTROLYTES 4.25/5

SULFITE-FREE

(4.25% Amino Acids
with Electrolytes in
5% Dextrose with
Calcium) Injection

CENTRL LINE INFUSION ONLY

1000 mL INJECTION PORT CHAMBER
10% Dextrose Injection with Calcium

1000 mL OUTLET PORT CHAMBER
8.5% Amino Acid Injection
with Electrolytes

Rx Only

ACTIVATE SEAL AND
MIX THOROUGHLY BEFORE USE

SEE PRESRCIBING INFORMATION FOR INSTRUCTIONS
ON ACTIVATION

AFTER MIXING THE PRODUCT REPRESENTS 2000 mL

REFRIGERATED STORAGE IS LIMITED TO
9 DAYS ONCE OVERWRAP IS OPENED

A SLIGHT YELLOW COLOR DOES NOT ALTER THE
QUALITY AND EFFICACY OF THIS PRODUCT

ASK PHARMACIST ABOUT ADDITIVE COMPATIBILITY

2D Datamatrix (GS1):
NDC, LOT, EXP

2D Datamatrix
Barcode

CONTENTS OF EACH 100 mL OF THE ADMIXED
INJECTION
DEXTROSE HYDROUS USP 5 g

ESSENTIAL AMINO ACIDS
LEUCINE 311 mg
ISOLEUCINE 255 mg
VALINE 247 mg
LYSINE (ADDED AS
THE HYDROCHLORIDE SALT) 247 mg
PHENYLALANINE 238 mg
HISTIDINE 204 mg
THREONINE 179 mg
METHIONINE 170 mg
TRYPTOPHAN 77 mg

NONESSENTIAL AMINO ACIDS
ALANINE 880 mg
ARGININE 489 mg
GLYCINE 438 mg
PROLINE 289 mg
SERINE 213 mg
TYROSINE 17 mg

ELECTROLYTES
SODIUM ACETATE
TRIHYDRATE USP 297 mg
DIBASIC POTASSIUM
PHOSPHATE USP 261 mg
SODIUM CHLORIDE USP 77 mg
MAGNESIUM CHLORIDE USP 51 mg
CALCIUM CHLORIDE
DIHYDRATE USP 33 mg

mEq/L
SODIUM 35
POTASSIUM 30
MAGNESIUM 5
CALCIUM 4.5 (2.2 mmol/L)
ACETATE 70
CHLORIDE 39
PHOSPHATE 30 (15 mmol/L)

BALANCED BY IONS FROM AMINO ACIDS
pH ADJUSTED WITH GLACIAL ACETIC ACID
AND HYDROCHLORIC ACID

STERILE
SINGLE DOSE CONTAINER

STORE AT ROOM TEMPERATURE (25°C/77°F)
IN UNOPENED OVERWRAP

AVOID EXCESSIVE HEAT

PROTECT FROM FREEZING

SEE PRESCRIBING INFORMATION

BAXTER LOGO
BAXTER HEALTHCARE CORPORATION
DEERFIELD IL 60015 USA
MADE IN BELGIUM

EXP LOT

2000

1600

1000

800

600

400

BE-35-05-065

200

Container Label

2B7740L
NDC 0338-7030-01
1000 mL

Bacode
(01) 00303387030012

CLINIMIX E
WITH ELECTROLYTES 5/15

SULFITE-FREE
(5% Amino Acid with Electrolytes in
15% Dextrose with Calcium) Injection

CENTRAL LINE INFUSION ONLY

500 mL INJECTION PORT CHAMBER
30% Dextrose Injection with Calcium

500 mL OUTLET PORT CHAMBER
10% Amino Acid Injection

Rx Only

2D Datamatrix (GS1):
NDC, LOT, EXP

2D Datamatrix
Barcode

ACTIVATE SEAL AND
MIX THOROUGHLY BEFORE USE

SEE PRESRCIBING INFORMATION FOR
INSTRUCTIONS ON ACTIVATION

AFTER MIXING THE PRODUCT
REPRESENTS 1000 mL

REFRIGERATED STORAGE IS LIMITED TO
9 DAYS ONCE OVERWRAP IS OPENED

A SLIGHT YELLOW COLOR DOES NOT
ALTER THE QUALITY AND EFFICACY OF
THIS PRODUCT

ASK PHARMACIST ABOUT ADDITIVE
COMPATIBILITY

CONTENTS OF EACH 100 mL OF THE ADMIXED
INJECTION
DEXTROSE HYDROUS USP 15 g

ESSENTIAL AMINO ACIDS
LEUCINE 365 mg
ISOLEUCINE 300 mg
VALINE 290 mg
LYSINE (ADDED AS THE
HYDROCHLORIDE SALT) 290 mg
PHENYLALANINE 280 mg
HISTIDINE 240 mg
THREONINE 210 mg
METHIONINE 200 mg
TRYPTOPHAN 90 mg

NONESSENTIAL AMINO ACIDS
ALANINE 1035 mg
ARGININE 575 mg
GLYCINE 515 mg
PROLINE 340 mg
SERINE 250 mg
TYROSINE 20 mg

ELECTROLYTES
SODIUM ACETATE TRIHYDRATE USP 340 mg
DIBASIC POTASSIUM PHOSPHATE USP 261 mg
SODIUM CHLORIDE USP 59 mg
MAGNESIUM CHLORIDE USP 51 mg
CALCIUM CHLORIDE DIHYDRATE USP 33 mg

mEq/L
SODIUM 35
POTASSIUM 30
MAGNESIUM 5
CALCIUM 4.5 (2.2 mmol/L)
ACETATE 80
CHLORIDE 39
PHOSPHATE 30 (15 mmol/L)

BALANCED BY IONS FROM AMINO ACIDS
pH ADJUSTED WITH GLACIAL ACETIC ACID
AND HYDROCHLORIC ACID

STERILE SINGLE DOSE CONTAINER

ROOM TEMPERATURE (25°C/77°F)
IN UNOPENED OVERWRAP
AVOID EXCESSIVE HEAT
PROTECT FROM FREEZING
SEE PRESCRIBING INFORMATION

BAXTER LOGO
BAXTER HEALTHCARE CORPORATION
DEERFIELD IL 60015 USA
MADE IN BELGIUM

EXP LOT

1600

1000

800

600

400

BE-35-05-071

200

Container Label

2B7721L
NDC 0338-7032-01
2000 mL

Barcode
(01) 00303387032016

CLINIMIX E
WITH ELECTROLYTES 5/15

SULFITE-FREE

(5% Amino Acids
with Electrolytes in
15% Dextrose with
Calcium) Injection

CENTRAL LINE INFUSION ONLY

1000 mL INJECTION PORT CHAMBER
30% Dextrose Injection with Calcium

1000 mL OUTLET PORT CHAMBER
10% Amino Acid Injection

Rx Only

ACTIVATE SEAL AND
MIX THOROUGHLY BEFORE USE

SEE PRESRCIBING INFORMATION FOR INSTRUCTIONS
ON ACTIVATION

AFTER MIXING THE PRODUCT REPRESENTS 2000 mL

REFRIGERATED STORAGE IS LIMITED TO
9 DAYS ONCE OVERWARP IS OPENED

A SLIGHT YELLOW COLOR DOES NOT ALTER THE
QUALITY AND EFFICACY OF THIS PRODUCT

ASK PHARMACIST ABOUT ADDITIVE COMPATIBILITY

2D Datamatrix (GS1):
NDC, LOT, EXP

2D Datamatrix
Barcode

CONTENTS OF EACH 100 mL OF THE ADMIXED
INJECTION
DEXTROSE HYDROUS USP 15

ESSENTIAL AMINO ACIDS
LEUCINE 365 mg
ISOLEUCINE 300 mg
VALINE 290 mg
LYSINE (ADDED AS THE
HYDROCHLORIDE SALT) 290 mg
PHENYLALANINE 280 mg
HISTIDINE 240 mg
THREONINE 210 mg
METHIONINE 200 mg
TRYPTOPHAN 90 mg

NONESSENTIAL AMINO ACIDS
ALANINE 1035 mg
ARGININE 575 mg
GLYCINE 515 mg
PROLINE 340 mg
SERINE 250 mg
TYROSINE 20 mg

ELECTROLYTES
SODIUM ACETATE
TRIHYDRATE USP 340 mg
DIBASIC POTASSIUM
PHOSPHATE USP 261 mg
SODIUM CHLORIDE USP 59 mg
MAGNESIUM CHLORIDE USP 51 mg
CALCIUM CHLORIDE DIHYDRATE USP 33 mg

mEq/L
SODIUM 35
POTASSIUM 30
MAGNESIUM 5
CALCIUM 4.5 (2.2 mmol/L)
ACETATE 80
CHLORIDE 39
PHOSPHATE 30 (15 mmol/L)

BALANCED BY IONS FROM AMINO ACIDS
pH ADJUSTED WITH GLACIAL ACETIC ACID
AND HYDROCHLORIC ACID

STERILE
SINGLE DOSE CONTAINER

ROOM TEMPERATURE (25°C/77°F)
IN UNOPENED OVERWRAP

AVOID EXCESSIVE HEAT

PROTECT FROM FREEZING

SEE PRESCRIBING INFORMATION

BAXTER LOGO
BAXTER HEALTHCARE CORPORATION
DEERFIELD IL 60015 USA
MADE IN BELGIUM

EXP LOT

2000

1600

1000

800

600

400

BE-35-05-066

200

Container Label

2B7741L
NDC 0338-7034-01
1000 mL

Barcode
(01) 00303387034010

CLINIMIX E
WITH ELECTROLYTES 5/20

SULFITE-FREE

(5% Amino Acids with Electrolytes in
20% Dextrose with Calcium) Injection

CENTRAL LINE INFUSION ONLY

500 mL INJECTION PORT CHAMBER
40% Dextrose Injection with Calcium

500 mL OUTLET PORT CHAMBER
10% Amino Acid Injection

Rx Only

2D Datamatrix (GS1):
NDC, LOT, EXP

2D Datamatrix
Barcode

ACTIVATE SEAL AND
MIX THOROUGHLY BEFORE USE

SEE PRESRCIBING INFORMATION FOR
INSTRUCTIONS ON ACTIVATION

AFTER MIXING THE PRODUCT
REPRESENTS 1000 mL

REFRIGERATED STORAGE IS LIMITED TO
9 DAYS ONCE OVERWRAP IS OPENED

A SLIGHT YELLOW COLOR DOES NOT
ALTER THE QUALITY AND EFFICACY OF
THIS PRODUCT

ASK PHARMACIST ABOUT ADDITIVE
COMPATIBILITY

CONTENTS OF EACH 100 mL OF THE ADMIXED INJECTION
DEXTROSE HYDROUS USP 20 g

ESSENTIAL AMINO ACIDS
LEUCINE 365 mg
ISOLEUCINE 300 mg
VALINE 290 mg
LYSINE (ADDED AS THE
HYDROCHLORIDE SALT) 290 mg
PHENYLALANINE 280 mg
HISTIDINE 240 mg
THREONINE 210 mg
METHIONINE 200 mg
TRYPTOPHAN 90 mg

NONESSENTIAL AMINO ACIDS
ALANINE 1035 mg
ARGININE 575 mg
GLYCINE 515 mg
PROLINE 340 mg
SERINE 250 mg
TYROSINE 20 mg

ELECTROLYTES
SODIUM ACETATE TRIHYDRATE USP 340 mg
DIBASIC POTASSIUM PHOSPHATE USP 261 mg
SODIUM CHLORIDE USP 59 mg
MAGNESIUM CHLORIDE USP 51 mg
CALCIUM CHLORIDE DIHYDRATE USP 33 mg

mEq/L
SODIUM 35
POTASSIUM 30
MAGNESIUM 5
CALCIUM 4.5 (2.2 mmol/L)
ACETATE 80
CHLORIDE 39
PHOSPHATE 30 (15 mmol/L)

BALANCED BY IONS FROM AMINO ACIDS
pH ADJUSTED WITH GLACIAL ACETIC ACID
AND HYDROCHLORIC ACID

STERILE SINGLE DOSE CONTAINER

ROOM TEMPERATURE (25°C/77°F)
IN UNOPENED OVERWRAP
AVOID EXCESSIVE HEAT
PROTECT FROM FREEZING
SEE PRESCRIBING INFORMATION

BAXTER LOGO
BAXTER HEALTHCARE CORPORATION
DEERFIELD IL 60015 USA
MADE IN BELGIUM

EXP LOT

1600

1000

800

600

400

BE-35-05-072

200

Container Label

2B7722L
NDC 0338-7036-01
2000 mL

Barcode
(01) 00303387032016

CLINIMIX E
WITH ELECTROLYTES 5/20

SULFITE-FREE

(5% Amino Acids
with Electrolytes in
20% Dextrose with
Calcium) Injection

CENTRAL LINE INFUSION ONLY

1000 mL INJECTION PORT CHAMBER
40% Dextrose Injection with Calcium

1000 mL OUTLET PORT CHAMBER
10% Amino Acid Injection

Rx Only

ACTIVATE SEAL AND
MIX THOROUGHLY BEFORE USE

SEE PRESRCIBING INFORMATION FOR INSTRUCTIONS
ON ACTIVATION

AFTER MIXING THE PRODUCT REPRESENTS 2000 mL

REFRIGERATED STORAGE IS LIMITED TO
9 DAYS ONCE OVERWRAP IS OPENED

A SLIGHT YELLOW COLOR DOES NOT ALTER THE
QUALITY AND EFFICACY OF THIS PRODUCT

ASK PHARMACIST ABOUT ADDITIVE COMPATIBILITY

2D Datamatrix (GS1):
NDC, LOT, EXP

2D Datamatrix
Barcode

CONTENTS OF EACH 100 mL OF THE ADMIXED
INJECTION
DEXTROSE HYDROUS USP 20 g

ESSENTIAL AMINO ACIDS
LEUCINE 365 mg
ISOLEUCINE 300 mg
VALINE 290 mg
LYSINE (ADDED AS THE
HYDROCHLORIDE SALT) 290 mg
PHENYLALANINE 280 mg
HISTIDINE 240 mg
THREONINE 210 mg
METHIONINE 200 mg
TRYPTOPHAN 90 mg

NONESSENTIAL AMINO ACIDS
ALANINE 1035 mg
ARGININE 575 mg
GLYCINE 515 mg
PROLINE 340 mg
SERINE 250 mg
TYROSINE 20 mg

ELECTROLYTES
SODIUM ACETATE
TRIHYDRATE USP 340 mg
DIBASIC POTASSIUM
PHOSPHATE USP 261 mg
SODIUM CHLORIDE USP 59 mg
MAGNESIUM CHLORIDE USP 51 mg
CALCIUM CHLORIDE
DIHYDRATE USP 33 mg

mEq/L
SODIUM 35
POTASSIUM 30
MAGNESIUM 5
CALCIUM 4.5 (2.2 mmol/L)
ACETATE 80
CHLORIDE 39
PHOSPHATE 30 (15 mmol/L)

BALANCED BY IONS FROM AMINO ACIDS
pH ADJUSTED WITH GLACIAL ACETIC ACID
AND HYDROCHLORIC ACID

STERILE
SINGLE DOSE CONTAINER

ROOM TEMPERATURE (25°C/77°F)
IN UNOPENED OVERWARP

AVOID EXCESSIVE HEAT

PROTECT FROM FREEZING

SEE PRESCRIBING INFORMATION

BAXTER LOGO
BAXTER HEALTHCARE CORPORATION
DEERFIELD IL 60015 USA
MADE IN BELGIUM

EXP LOT

2000

1600

1000

800

600

400

BE-35-05-066

200